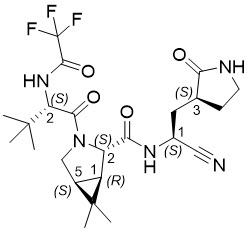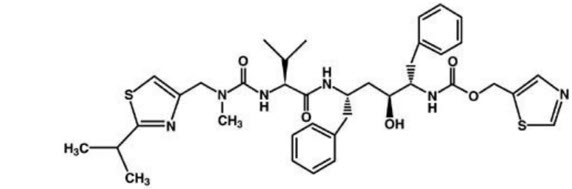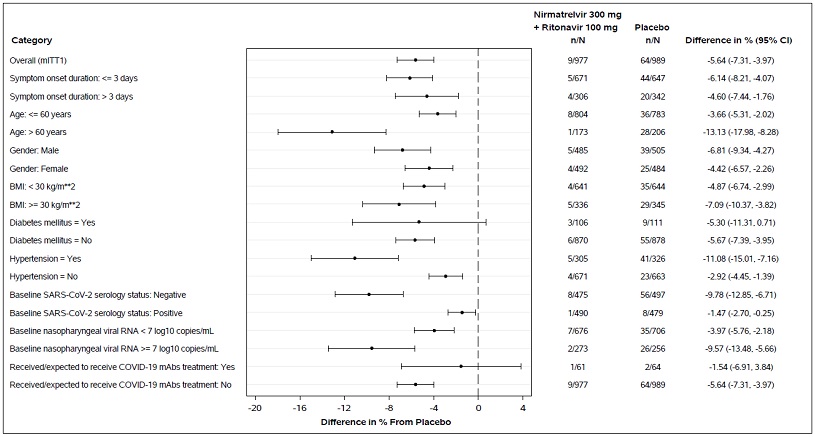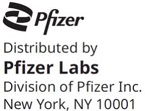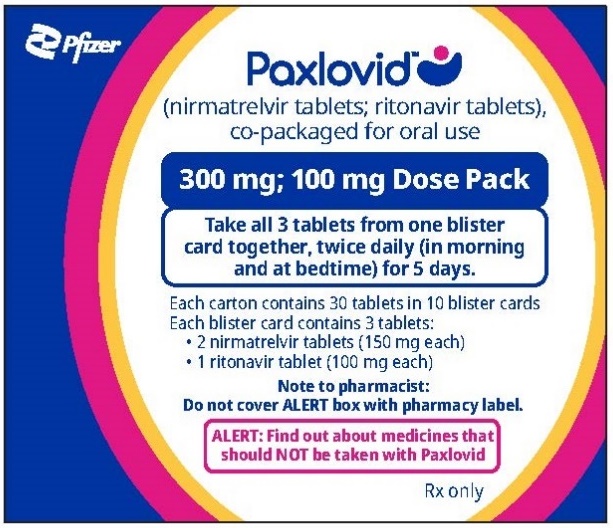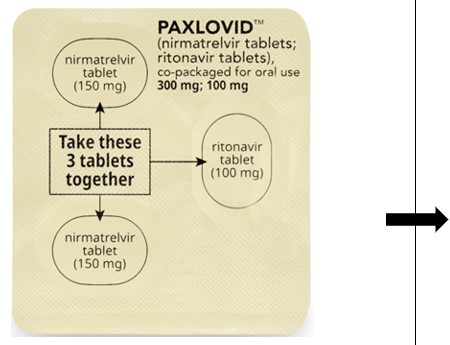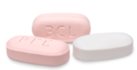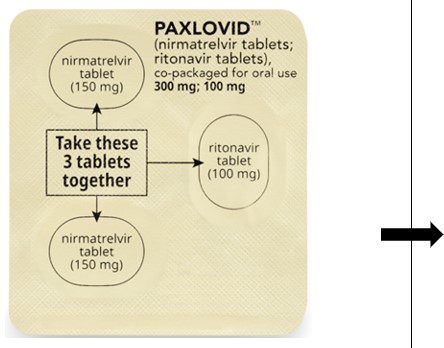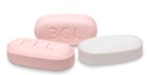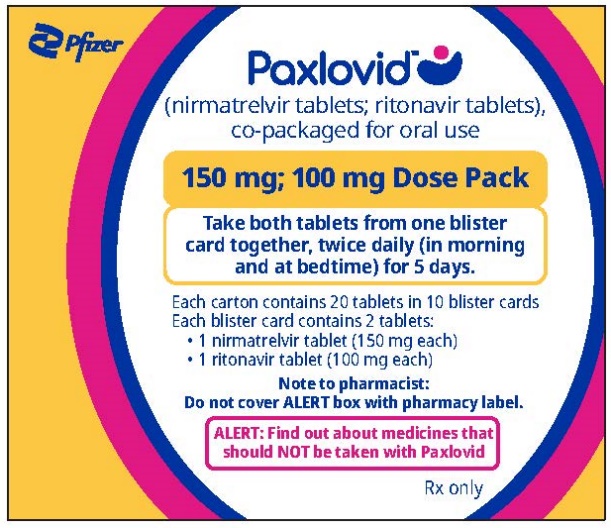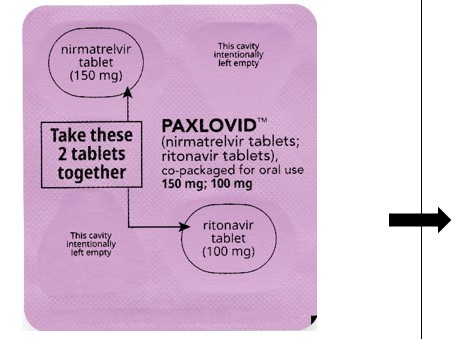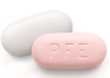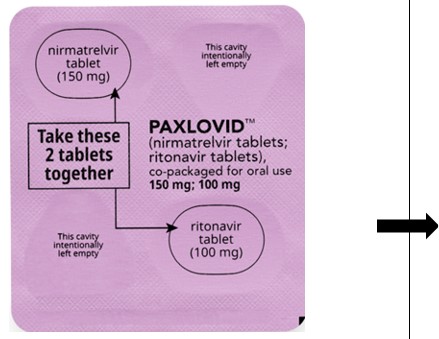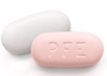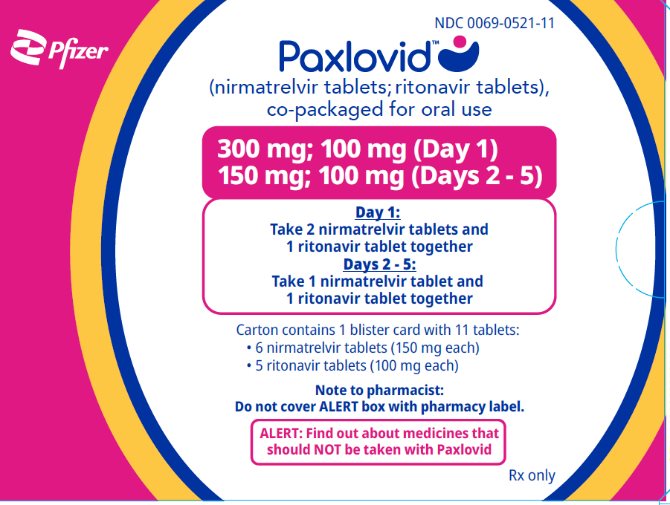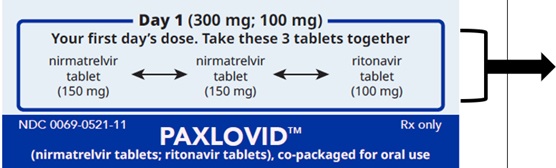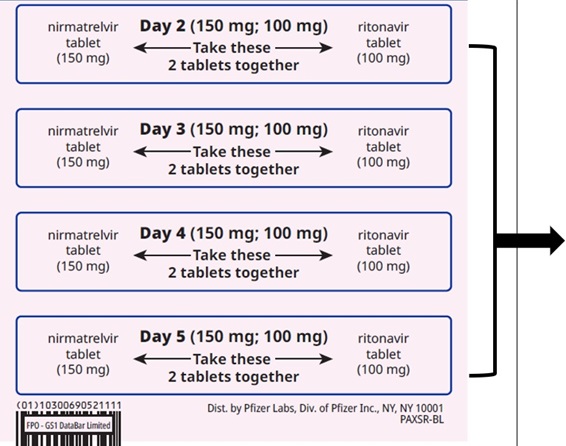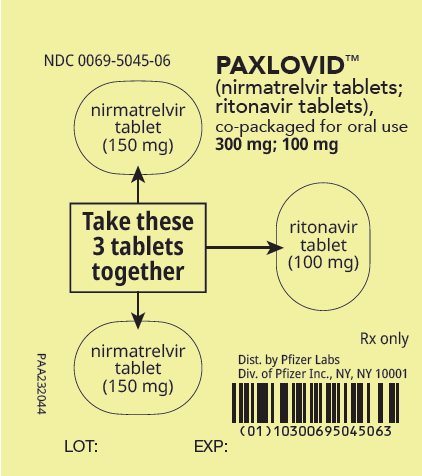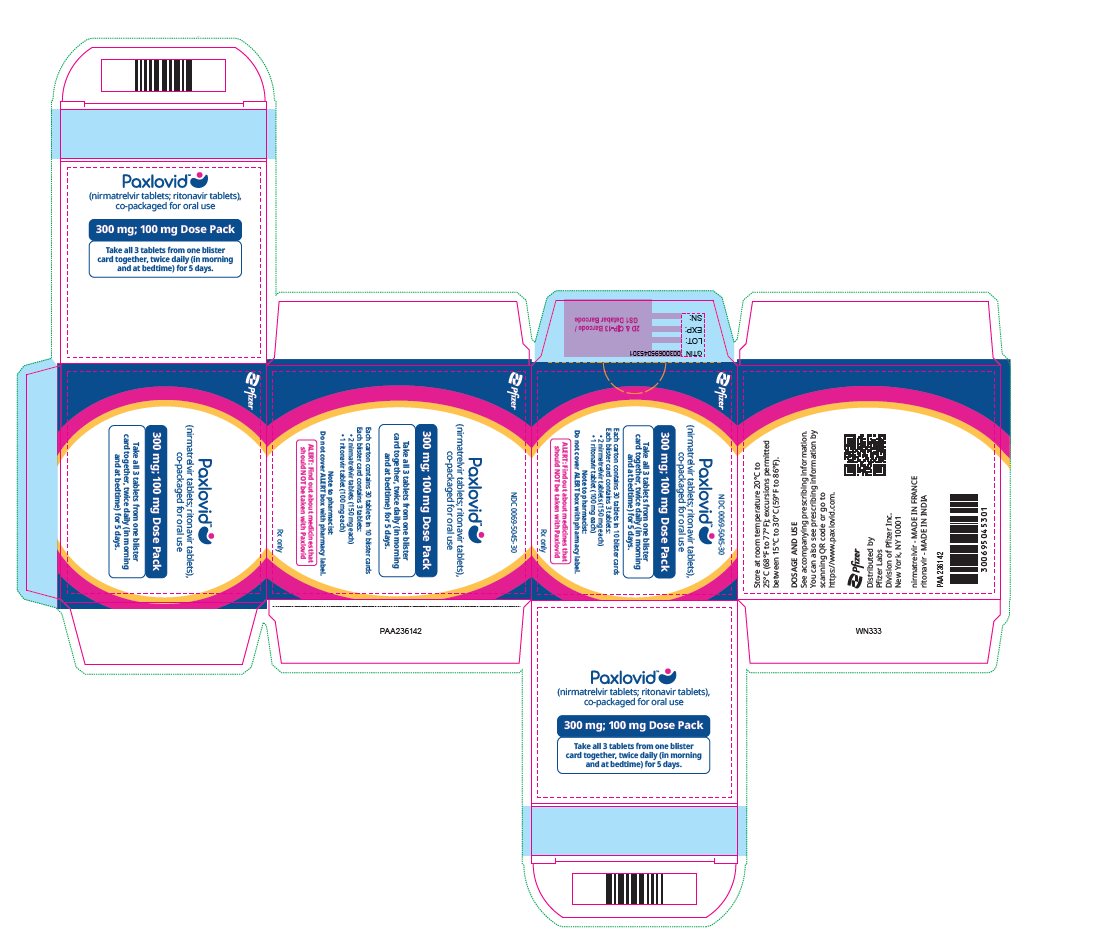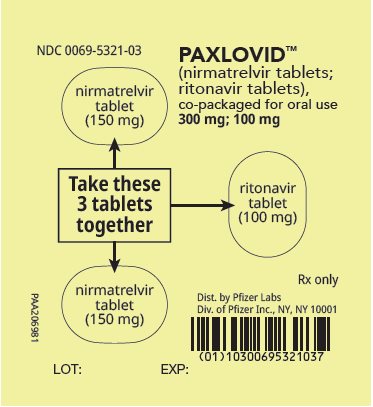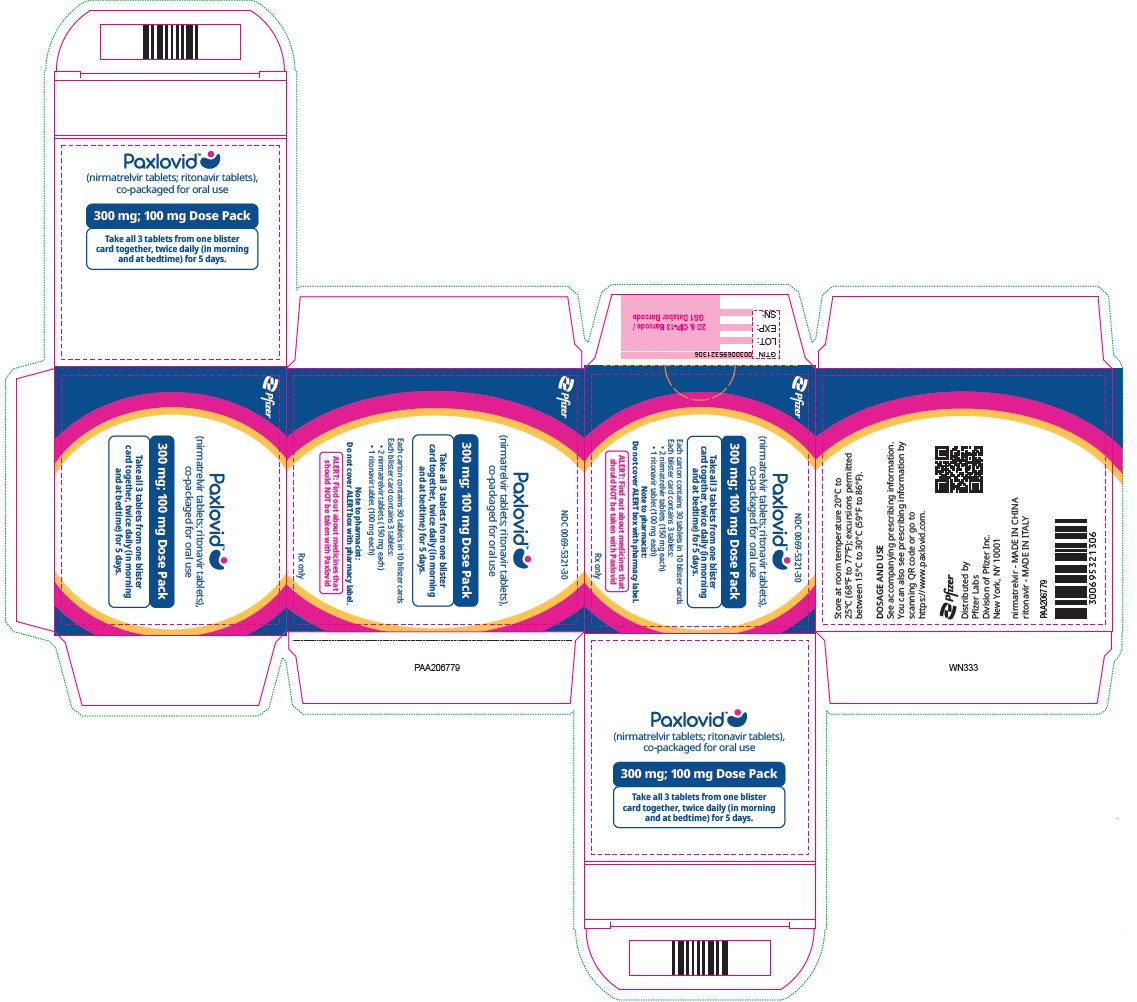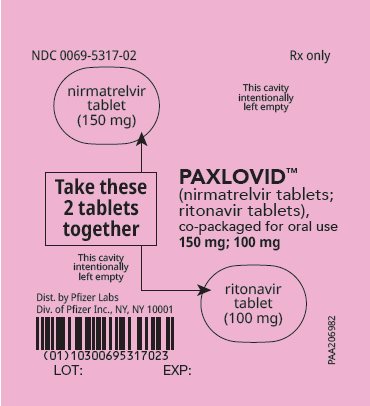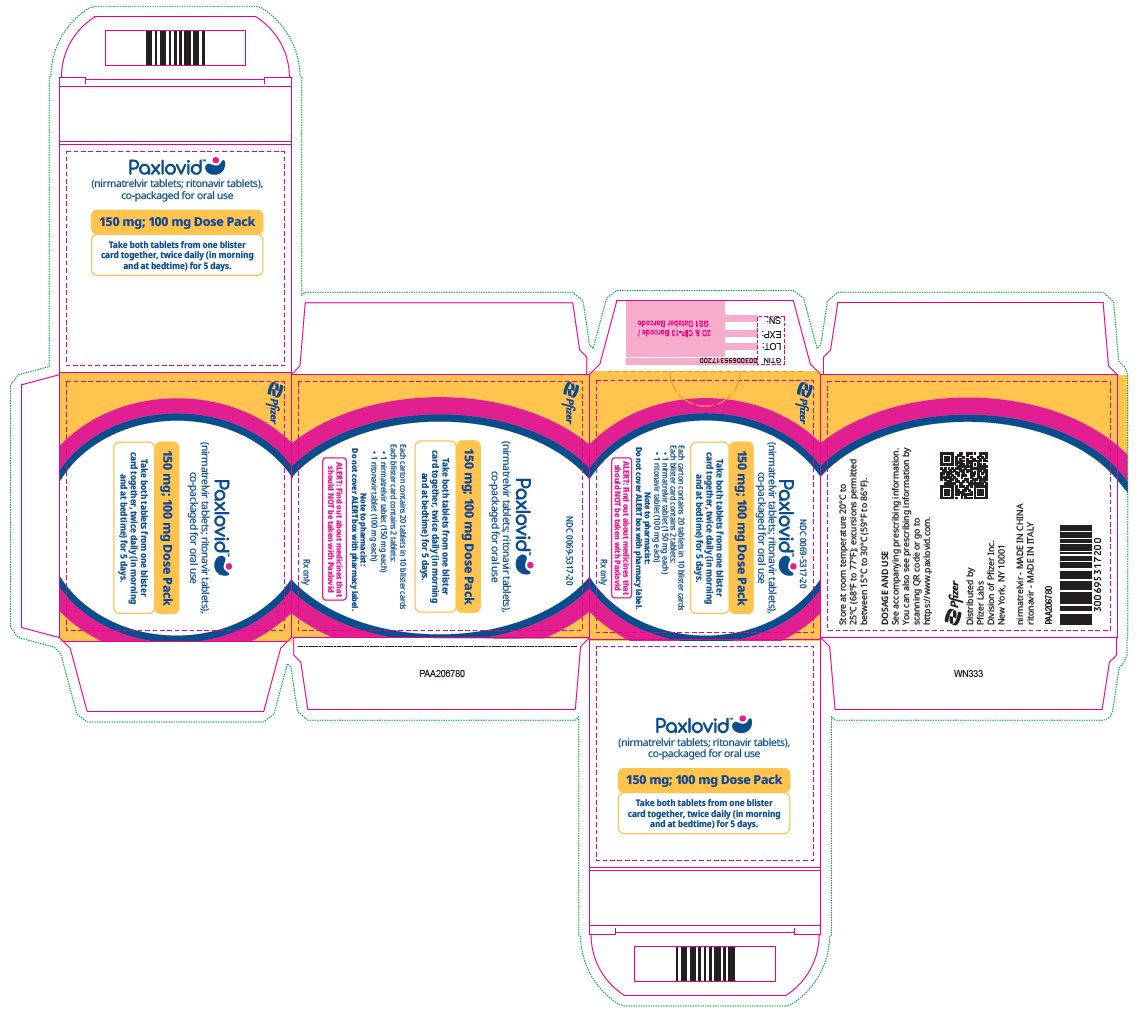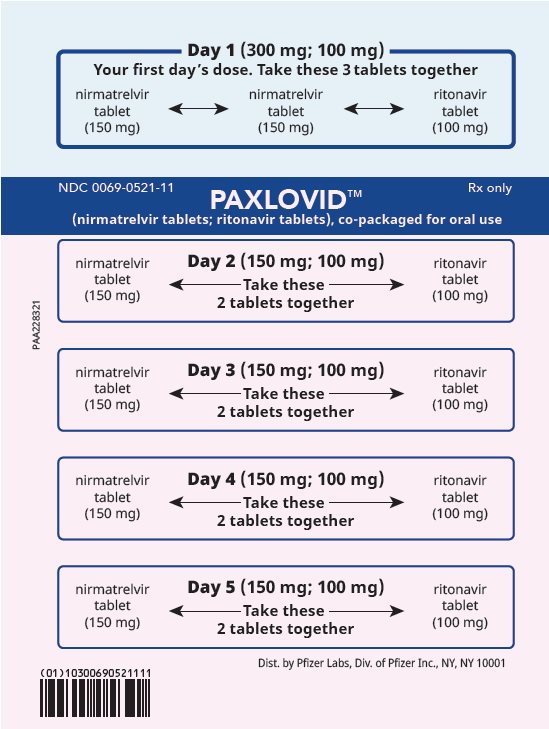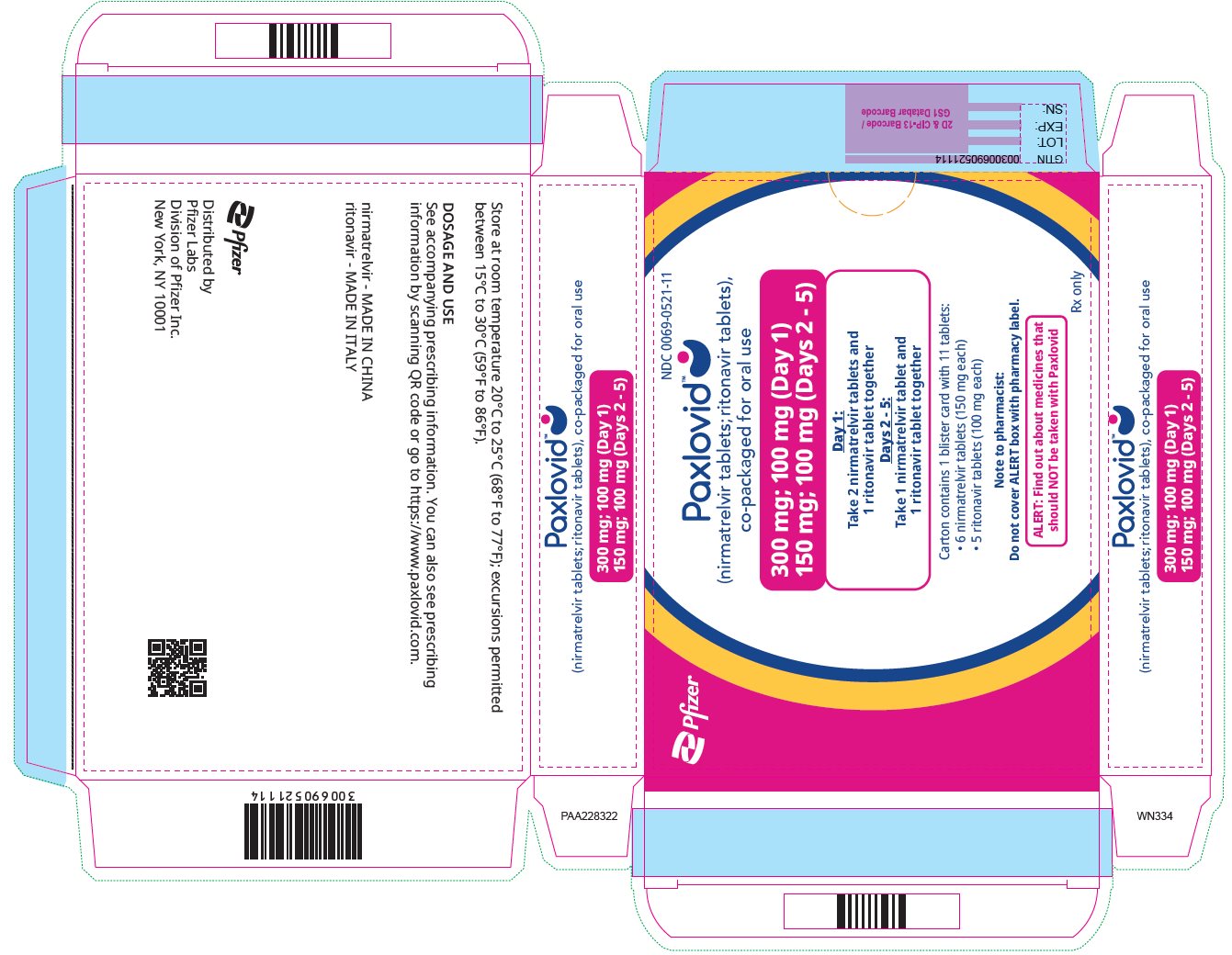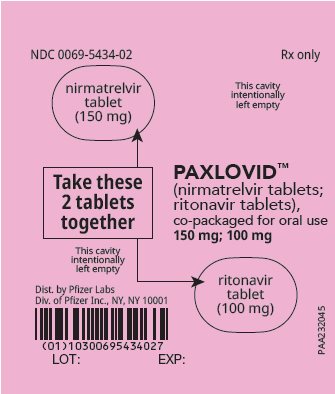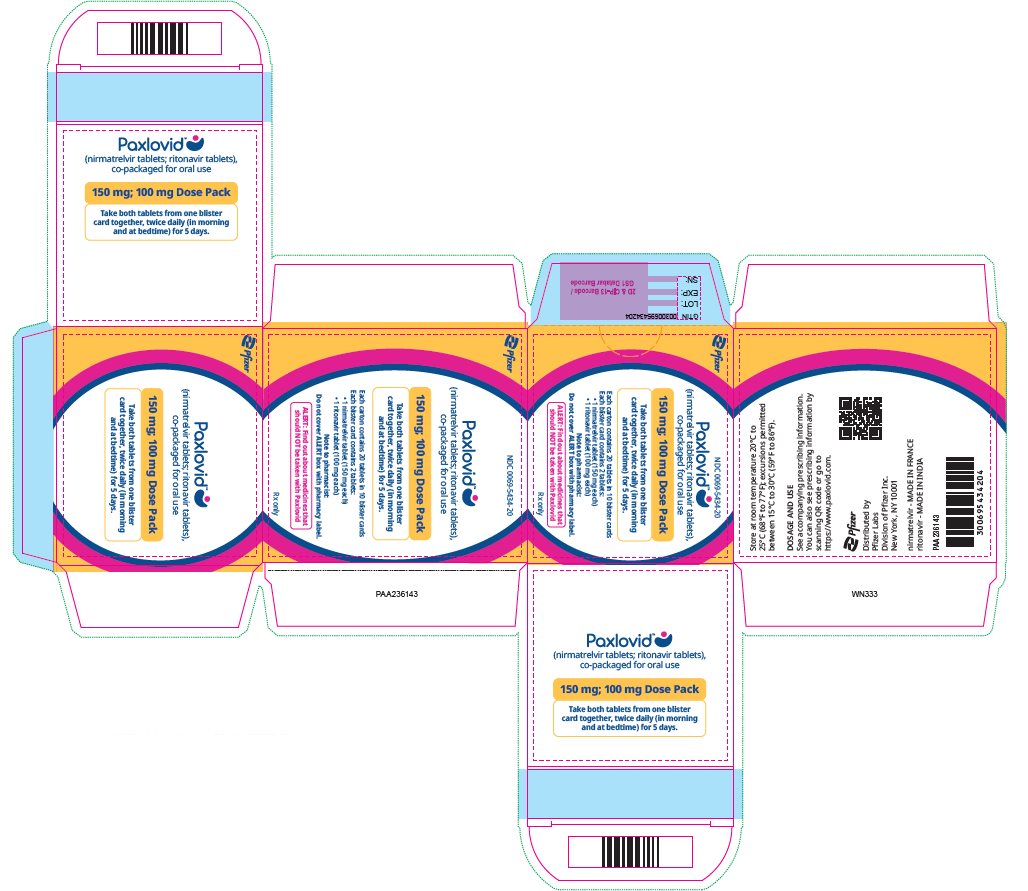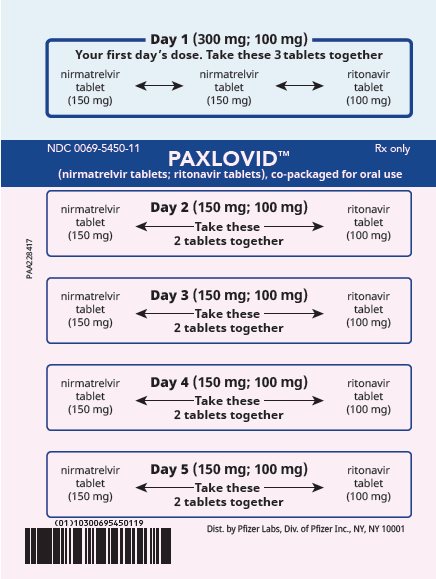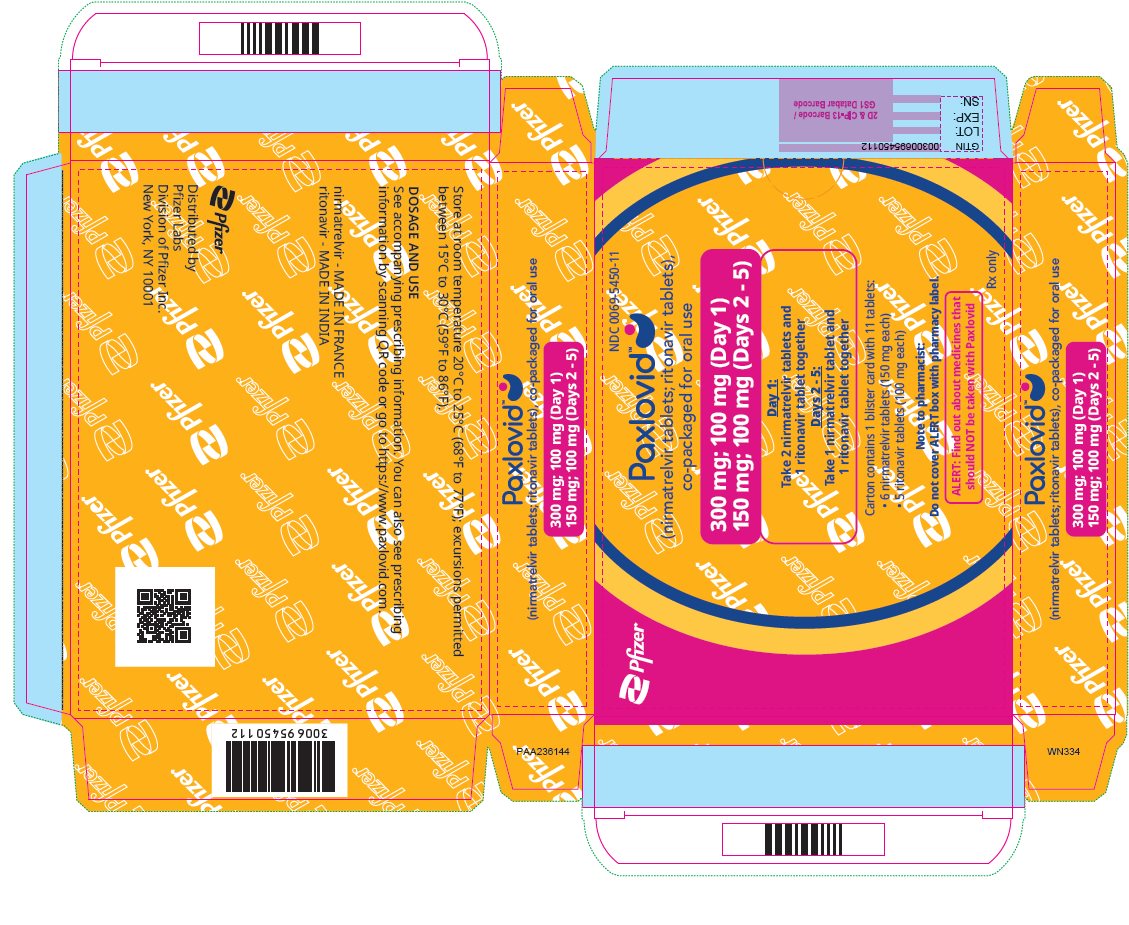 DRUG LABEL: Paxlovid
NDC: 0069-5045 | Form: KIT | Route: ORAL
Manufacturer: Pfizer Laboratories Div Pfizer Inc
Category: prescription | Type: HUMAN PRESCRIPTION DRUG LABEL
Date: 20260219

ACTIVE INGREDIENTS: NIRMATRELVIR 150 mg/1 1; RITONAVIR 100 mg/1 1
INACTIVE INGREDIENTS: SILICON DIOXIDE; CROSCARMELLOSE SODIUM; LACTOSE MONOHYDRATE; MICROCRYSTALLINE CELLULOSE; SODIUM STEARYL FUMARATE; HYPROMELLOSE 2910 (10000 MPA.S); FERRIC OXIDE RED; POLYETHYLENE GLYCOL, UNSPECIFIED; TITANIUM DIOXIDE; ANHYDROUS DIBASIC CALCIUM PHOSPHATE; SILICON DIOXIDE; COPOVIDONE K25-31; SODIUM STEARYL FUMARATE; SORBITAN MONOLAURATE; HYDROXYPROPYL CELLULOSE (1600000 WAMW); HYPROMELLOSE 2910 (6 MPA.S); POLYETHYLENE GLYCOL 400; POLYETHYLENE GLYCOL 3350; POLYSORBATE 80; TALC; TITANIUM DIOXIDE

HIGHLIGHTS OF PRESCRIBING INFORMATION

These highlights do not include all the information needed to use PAXLOVID safely and effectively. See full prescribing information for PAXLOVID.
PAXLOVIDTM (nirmatrelvir tablets; ritonavir tablets), co-packaged for oral use
Initial U.S. Approval: 2023

RECENT MAJOR CHANGES

Contraindications (4) | 02/2026

WARNING: SIGNIFICANT DRUG INTERACTIONS WITH PAXLOVID

See full prescribing information for complete boxed warning.

- PAXLOVID includes ritonavir, a strong CYP3A inhibitor, which may lead to greater exposure of certain concomitant medications, resulting in potentially severe, life-threatening, or fatal events. (4, 5.1, 7)
- Prior to prescribing PAXLOVID: 1) Review all medications taken by the patient to assess potential drug-drug interactions with a strong CYP3A inhibitor like PAXLOVID and 2) Determine if concomitant medications require a dose adjustment, interruption, and/or additional monitoring. (7)
- Consider the benefit of PAXLOVID treatment in reducing hospitalization and death, and whether the risk of potential drug-drug interactions for an individual patient can be appropriately managed. (5.1, 7, 14)

1 INDICATIONS AND USAGE

PAXLOVID which includes nirmatrelvir, a severe acute respiratory syndrome coronavirus 2 (SARS-CoV-2) main protease (Mpro: also referred to as 3CLpro or nsp5 protease) inhibitor, and ritonavir, an HIV-1 protease inhibitor and CYP3A inhibitor, is indicated for the treatment of mild-to-moderate coronavirus disease 2019 (COVID-19) in adults who are at high risk for progression to severe COVID-19, including hospitalization or death. (1)
Limitations of Use

PAXLOVID is not approved for use as pre-exposure or post-exposure prophylaxis for prevention of COVID-19. (1)

2 DOSAGE AND ADMINISTRATION

PAXLOVID is nirmatrelvir tablets co-packaged with ritonavir tablets. (2.1)

Nirmatrelvir must be co-administered with ritonavir. (2.1)

- Initiate PAXLOVID treatment as soon as possible after diagnosis of COVID-19 and within 5 days of symptom onset. (2.1)
- Administer orally with or without food. (2.1)
- Administer at approximately the same time each day. (2.2, 2.3)
- Dosage: 300 mg nirmatrelvir (two 150 mg tablets) with 100 mg ritonavir (one 100 mg tablet), with all 3 tablets taken together twice daily for 5 days. (2.2)
- Dose Reduction for Renal Impairment (2.3, 8.6, 12.3)

Renal Function | Days of Treatment | Dose and Dose Frequency [PAXLOVID should be administered at approximately the same time each day for 5 days.]
Moderate renal impairment (eGFR ≥30 to <60 mL/min) | Days 1-5 | 150 mg nirmatrelvir (one 150 mg tablet) with 100 mg ritonavir (one 100 mg tablet) twice daily
Severe renal impairment (eGFR <30 mL/min) including those requiring hemodialysis [On days of hemodialysis, the PAXLOVID dose should be administered after hemodialysis.] | Day 1 | 300 mg nirmatrelvir (two 150 mg tablets) with 100 mg ritonavir (one 100 mg tablet) once
Severe renal impairment (eGFR <30 mL/min) including those requiring hemodialysis [On days of hemodialysis, the PAXLOVID dose should be administered after hemodialysis.] | Days 2-5 | 150 mg nirmatrelvir (one 150 mg tablet) with 100 mg ritonavir (one 100 mg tablet) once daily
Abbreviation: eGFR=estimated glomerular filtration rate.

- PAXLOVID is not recommend in patients with severe hepatic impairment (Child-Pugh Class C). (2.4, 8.7)

3 DOSAGE FORMS AND STRENGTHS

- Tablets: nirmatrelvir 150 mg (3)
- Tablets: ritonavir 100 mg (3)

4 CONTRAINDICATIONS

- History of clinically significant hypersensitivity reactions to the active ingredients (nirmatrelvir or ritonavir) or any other components. (4)
- Co-administration with drugs highly dependent on CYP3A for clearance and for which elevated concentrations are associated with serious and/or life-threatening reactions. (4, 7.3)
- Co-administration with potent CYP3A inducers where significantly reduced nirmatrelvir or ritonavir plasma concentrations may be associated with the potential for loss of virologic response and possible resistance. (4, 7.3)

5 WARNINGS AND PRECAUTIONS

- The concomitant use of PAXLOVID and certain other drugs may result in potentially significant drug interactions. Consult the Full Prescribing Information prior to and during treatment for potential drug interactions. (5.1, 7)
- Hypersensitivity Reactions: Anaphylaxis, serious skin reactions (including toxic epidermal necrolysis and Stevens-Johnson syndrome), and other hypersensitivity reactions have been reported with PAXLOVID. If signs and symptoms of a clinically significant hypersensitivity reaction or anaphylaxis occur, immediately discontinue PAXLOVID and initiate appropriate medications and/or supportive care. (5.2)
- Hepatotoxicity: Hepatic transaminase elevations, clinical hepatitis, and jaundice have occurred in patients receiving ritonavir. (5.3)
- HIV-1 Drug Resistance: PAXLOVID use may lead to a risk of HIV-1 developing resistance to HIV protease inhibitors in individuals with uncontrolled or undiagnosed HIV-1 infection. (5.4)

6 ADVERSE REACTIONS

Most common adverse reactions (incidence ≥1% and greater incidence than in the placebo group) are dysgeusia and diarrhea. (6.1)

To report SUSPECTED ADVERSE REACTIONS, contact Pfizer Inc. at 1-800-438-1985 or FDA at 1-800-FDA-1088 or www.fda.gov/medwatch.

7 DRUG INTERACTIONS

Co-administration of PAXLOVID can alter the plasma concentrations of other drugs and other drugs may alter the plasma concentrations of PAXLOVID. Consider the potential for drug interactions prior to and during PAXLOVID therapy and review concomitant medications during PAXLOVID therapy. (4, 5.1, 7, 12.3)

FULL PRESCRIBING INFORMATION

WARNING: SIGNIFICANT DRUG INTERACTIONS WITH PAXLOVID

- PAXLOVID includes ritonavir, a strong CYP3A inhibitor, which may lead to greater exposure of certain concomitant medications, resulting in potentially severe, life-threatening, or fatal events [see Contraindications (4), Warnings and Precautions (5.1), and Drug Interactions (7)].
- Prior to prescribing PAXLOVID: 1) Review all medications taken by the patient to assess potential drug-drug interactions with a strong CYP3A inhibitor like PAXLOVID and 2) Determine if concomitant medications require a dose adjustment, interruption, and/or additional monitoring [see Drug Interactions (7)].
- Consider the benefit of PAXLOVID treatment in reducing hospitalization and death, and whether the risk of potential drug-drug interactions for an individual patient can be appropriately managed [see Warnings and Precautions (5.1), Drug Interactions (7), and Clinical Studies (14)].

1 INDICATIONS AND USAGE

PAXLOVID is indicated for the treatment of mild-to-moderate coronavirus disease 2019 (COVID-19) in adults who are at high risk for progression to severe COVID-19, including hospitalization or death.

Limitations of Use

PAXLOVID is not approved for use as pre-exposure or post-exposure prophylaxis for prevention of COVID-19 [see Clinical Studies (14.3)].

2 DOSAGE AND ADMINISTRATION

2.1 Important Dosage and Administration Information

PAXLOVID is nirmatrelvir tablets co-packaged with ritonavir tablets. There are three different dose packs available:

- PAXLOVID (nirmatrelvir; ritonavir) co-packaged for oral use 300 mg;100 mg [see Dosage and Administration (2.2)].
- PAXLOVID (nirmatrelvir; ritonavir) co-packaged for oral use 150 mg;100 mg for patients with moderate renal impairment [see Dosage and Administration (2.3)].
- PAXLOVID (nirmatrelvir; ritonavir) co-packaged for oral use 300 mg;100 mg (Day 1) and 150 mg;100 mg (Days 2-5) for patients with severe renal impairment [see Dosage and Administration (2.3)].

Nirmatrelvir must be co-administered with ritonavir. Failure to correctly co-administer nirmatrelvir with ritonavir may result in plasma levels of nirmatrelvir that are insufficient to achieve the desired therapeutic effect.

Prescriptions should specify the numeric dose of each active ingredient within PAXLOVID [see Dosage and Administration (2.2, 2.3)]. Completion of the full 5-day treatment course and continued isolation in accordance with public health recommendations are important to maximize viral clearance and minimize transmission of SARS-CoV-2.

The 5-day treatment course of PAXLOVID should be initiated as soon as possible after a diagnosis of COVID-19 has been made, and within 5 days of symptom onset even if baseline COVID-19 symptoms are mild. Should a patient require hospitalization due to severe or critical COVID-19 after starting treatment with PAXLOVID, the patient should complete the full 5-day treatment course per the healthcare provider's discretion.

If the patient misses a dose of PAXLOVID within 8 hours of the time it is usually taken, the patient should take it as soon as possible and resume the normal dosing schedule. If the patient misses a dose by more than 8 hours, the patient should not take the missed dose and instead take the next dose at the regularly scheduled time. The patient should not double the dose to make up for a missed dose.

PAXLOVID (both nirmatrelvir and ritonavir tablets) can be taken with or without food [see Clinical Pharmacology (12.3)]. The tablets should be swallowed whole and not chewed, broken, or crushed.

2.2 Recommended Dosage

The recommended dosage for PAXLOVID is 300 mg nirmatrelvir (two 150 mg tablets) with 100 mg ritonavir (one 100 mg tablet) with all 3 tablets taken together orally twice daily in the morning and at bedtime for 5 days.

2.3 Dosage in Patients with Renal Impairment

Prescriptions should specify the numeric dose of each active ingredient within PAXLOVID. Providers should counsel patients about renal dosing instructions [see Patient Counseling Information (17)].

No dosage adjustment is recommended in patients with mild renal impairment [estimated glomerular filtration rate (eGFR) ≥60 to <90 mL/min].

In patients with moderate renal impairment (eGFR ≥30 to <60 mL/min) or with severe renal impairment (eGFR <30 mL/min) including those requiring hemodialysis, the dosage of PAXLOVID should be reduced as shown in Table 1. PAXLOVID should be administered at approximately the same time each day for 5 days. On days patients with severe renal impairment undergo hemodialysis, the PAXLOVID dose should be administered after hemodialysis [see Use in Specific Populations (8.6), Clinical Pharmacology (12.3), and How Supplied/Storage and Handling (16)].

Table 1: Recommended Dose and Regimen for Patients with Renal Impairment

Renal Function | Days of Treatment | Dose and Dose Frequency [PAXLOVID should be administered at approximately the same time each day for 5 days.]
Moderate renal impairment (eGFR ≥30 to <60 mL/min) | Days 1-5 | 150 mg nirmatrelvir (one 150 mg tablet) with 100 mg ritonavir (one 100 mg tablet) twice daily
Severe renal impairment (eGFR <30 mL/min) including those requiring hemodialysis [On days of hemodialysis, the PAXLOVID dose should be administered after hemodialysis.] | Day 1 | 300 mg nirmatrelvir (two 150 mg tablets) with 100 mg ritonavir (one 100 mg tablet) once
Severe renal impairment (eGFR <30 mL/min) including those requiring hemodialysis [On days of hemodialysis, the PAXLOVID dose should be administered after hemodialysis.] | Days 2-5 | 150 mg nirmatrelvir (one 150 mg tablet) with 100 mg ritonavir (one 100 mg tablet) once daily
Abbreviation: eGFR=estimated glomerular filtration rate.

2.4 Use in Patients with Hepatic Impairment

No dosage adjustment is needed in patients with mild (Child-Pugh Class A) or moderate (Child-Pugh Class B) hepatic impairment.

No pharmacokinetic or safety data are available regarding the use of nirmatrelvir or ritonavir in subjects with severe (Child-Pugh Class C) hepatic impairment; therefore, PAXLOVID is not recommended for use in patients with severe hepatic impairment [see Use in Specific Populations (8.7)].

3 DOSAGE FORMS AND STRENGTHS

PAXLOVID is nirmatrelvir tablets co-packaged with ritonavir tablets [see How Supplied/Storage and Handling (16)].

- Nirmatrelvir is supplied as oval, pink immediate-release, film-coated tablets debossed with "PFE" on one side and "3CL" on the other side. Each tablet contains 150 mg of nirmatrelvir.
- Ritonavir is supplied as white or white to off-white film-coated tablets uniquely identified by the color, shape, and debossing. Each tablet contains 100 mg of ritonavir.

4 CONTRAINDICATIONS

PAXLOVID is contraindicated in patients with a history of clinically significant hypersensitivity reactions [e.g., toxic epidermal necrolysis (TEN) or Stevens-Johnson syndrome] to its active ingredients (nirmatrelvir or ritonavir) or any other components of the product.

PAXLOVID is contraindicated with drugs that are primarily metabolized by CYP3A and for which elevated concentrations are associated with serious and/or life-threatening reactions and drugs that are strong CYP3A inducers where significantly reduced nirmatrelvir or ritonavir plasma concentrations may be associated with the potential for loss of virologic response and possible resistance. There are certain other drugs for which concomitant use with PAXLOVID should be avoided and/or dose adjustment, interruption, or therapeutic monitoring is recommended. Drugs listed in this section are a guide and not considered a comprehensive list of all drugs that may be contraindicated with PAXLOVID. The healthcare provider should consult other appropriate resources such as the prescribing information for the interacting drug for comprehensive information on dosing or monitoring with concomitant use of a strong CYP3A inhibitor like PAXLOVID [see Drug Interactions (7.3)]:

➢ Drugs that are primarily metabolized by CYP3A for which elevated concentrations are associated with serious and/or life-threatening reactions [see Drug Interactions (7.3)]:
  - Alpha 1-adrenoreceptor antagonist: alfuzosin
  - Antianginal: ranolazine
  - Antiarrhythmic: amiodarone, dronedarone, flecainide, propafenone, quinidine
  - Anti-gout: colchicine (in patients with renal and/or hepatic impairment [see Table 2, Drug Interactions (7.3)])
  - Antipsychotics: lurasidone, pimozide
  - Benign prostatic hyperplasia agents: silodosin
  - Cardiovascular agents: eplerenone, ivabradine
  - Ergot derivatives: dihydroergotamine, ergotamine, methylergonovine
  - HMG-CoA reductase inhibitors: lovastatin, simvastatin (these drugs can be temporarily discontinued to allow PAXLOVID use [see Table 2, Drug Interactions (7.3)])
  - Immunosuppressants: voclosporin
  - Microsomal triglyceride transfer protein inhibitor: lomitapide
  - Migraine medications: eletriptan, ubrogepant
  - Mineralocorticoid receptor antagonists: finerenone
  - Non-opioid analgesic (selective blocker of Nav1.8 sodium channels): suzetrigine
  - Opioid antagonists: naloxegol
  - PDE5 inhibitor: sildenafil (Revatio®) when used for pulmonary arterial hypertension (PAH)
  - Sedative/hypnotics: triazolam, oral midazolam
  - Serotonin receptor 1A agonist/serotonin receptor 2A antagonist: flibanserin
  - Vasopressin receptor antagonists: tolvaptan
➢ Drugs that are strong CYP3A inducers where significantly reduced nirmatrelvir or ritonavir plasma concentrations may be associated with the potential for loss of virologic response and possible resistance. PAXLOVID cannot be started immediately after discontinuation of any of the following medications due to the delayed offset of the recently discontinued CYP3A inducer [see Drug Interactions (7.3)]:
  - Anticancer drugs: apalutamide, enzalutamide
  - Anticonvulsant: carbamazepine, phenobarbital, primidone, phenytoin
  - Antimycobacterials: rifampin, rifapentine
  - Cystic fibrosis transmembrane conductance regulator potentiators: lumacaftor/ivacaftor
  - Herbal products: St. John's Wort (hypericum perforatum)

5 WARNINGS AND PRECAUTIONS

5.1 Risk of Serious Adverse Reactions Due to Drug Interactions

Initiation of PAXLOVID, which contains ritonavir, a strong CYP3A inhibitor, in patients receiving medications metabolized by CYP3A or initiation of medications metabolized by CYP3A in patients already receiving PAXLOVID, may increase plasma concentrations of medications metabolized by CYP3A. Medications that induce CYP3A may decrease concentrations of PAXLOVID. These interactions may lead to:

- Clinically significant adverse reactions, potentially leading to severe, life-threatening, or fatal events from greater exposures of concomitant medications.
- Loss of therapeutic effect of PAXLOVID and possible development of viral resistance.

Severe, life-threatening, and/or fatal adverse reactions due to drug interactions have been reported in patients treated with PAXLOVID. The most commonly reported concomitant medications resulting in serious adverse reactions were calcineurin inhibitors (e.g., tacrolimus, cyclosporine), followed by calcium channel blockers.

Prior to prescribing PAXLOVID, review all medications taken by the patient to assess potential drug-drug interactions and determine if concomitant medications require a dose adjustment, interruption, and/or additional monitoring (e.g., calcineurin inhibitors) [see Contraindications (4) and Drug Interactions (7)]. See Table 2 for clinically significant drug interactions, including contraindicated drugs. Drugs listed in Table 2 are a guide and not considered a comprehensive list of all possible drugs that may interact with PAXLOVID.

Consider the benefit of PAXLOVID treatment in reducing hospitalization and death, and whether the risk of potential drug-drug interactions for an individual patient can be appropriately managed [see Drug Interactions (7) and Clinical Studies (14)].

5.2 Hypersensitivity Reactions

Anaphylaxis, serious skin reactions (including toxic epidermal necrolysis and Stevens-Johnson syndrome), and other hypersensitivity reactions have been reported with PAXLOVID [see Adverse Reactions (6.1)]. If signs and symptoms of a clinically significant hypersensitivity reaction or anaphylaxis occur, immediately discontinue PAXLOVID and initiate appropriate medications and/or supportive care.

5.3 Hepatotoxicity

Hepatic transaminase elevations, clinical hepatitis, and jaundice have occurred in patients receiving ritonavir. Therefore, caution should be exercised when administering PAXLOVID to patients with pre-existing liver diseases, liver enzyme abnormalities, or hepatitis.

5.4 Risk of HIV-1 Resistance Development

Because nirmatrelvir is co-administered with ritonavir, there may be a risk of HIV-1 developing resistance to HIV protease inhibitors in individuals with uncontrolled or undiagnosed HIV-1 infection [see Contraindications (4) and Drug Interactions (7)].

6 ADVERSE REACTIONS

The following clinically significant adverse reactions are described elsewhere in the labeling:

- Hypersensitivity reactions [see Warnings and Precautions (5.2)]

6.1 Clinical Trials Experience

Because clinical trials are conducted under widely varying conditions, adverse reaction rates observed in the clinical trials of a drug cannot be directly compared to rates in the clinical trials of another drug and may not reflect the rates observed in practice.

The safety of PAXLOVID is based on two Phase 2/3 randomized, placebo-controlled trials in symptomatic adult subjects 18 years of age and older with a laboratory confirmed diagnosis of SARS-CoV-2 infection. Subjects in both studies received PAXLOVID (nirmatrelvir/ritonavir 300 mg/100 mg) or placebo every 12 hours for 5 days for the treatment of mild-to-moderate COVID-19 within 5 days of symptom onset [see Clinical Studies (14)]:

- Trial C4671005 (EPIC-HR) enrolled subjects who were at high risk for progression to severe disease.
- Trial C4671002 (EPIC-SR) enrolled subjects who were at standard risk for progression to severe disease (previously unvaccinated subjects at standard risk or fully vaccinated subjects with at least 1 risk factor for progression to severe disease).

Adverse reactions were those reported while subjects were on study medication and through 28 days after the last dose of study treatment.

In Trial C4671005 (EPIC-HR), 1,038 subjects received PAXLOVID and 1,053 subjects received placebo. The most common adverse reactions (≥1% incidence in the PAXLOVID group and occurring at a greater frequency than in the placebo group) were dysgeusia (5% and <1%, respectively) and diarrhea (3% and 2%, respectively).

Among vaccinated or unvaccinated subjects at standard risk or fully vaccinated subjects with at least 1 risk factor for progression to severe disease in Trial C4671002 (EPIC-SR), 540 subjects received PAXLOVID and 528 subjects received placebo. The adverse reactions observed were consistent with those observed in EPIC-HR.

Trial C4671028 (EPIC-SRI) was a Phase 1, open-label trial that evaluated the effects of severe renal impairment on the pharmacokinetics, safety, and tolerability of PAXLOVID in non-hospitalized adult participants with COVID-19 and severe renal impairment. A total of 15 subjects with severe renal impairment were enrolled in this trial, with 12 subjects receiving intermittent hemodialysis and 3 subjects not on hemodialysis. Subjects received nirmatrelvir/ritonavir 300 mg/100 mg once on Day 1 followed by nirmatrelvir/ritonavir 150 mg/100 mg once daily from Days 2-5. The safety profile of PAXLOVID in subjects with severe renal impairment, including those requiring hemodialysis, was consistent with the safety profile observed in the Phase 2/3 randomized, placebo-controlled trials.

Emergency Use Authorization Experience in Subjects with COVID-19

The following adverse reactions have been identified during use of PAXLOVID under Emergency Use Authorization.

Immune System Disorders: Anaphylaxis, hypersensitivity reactions [see Warnings and Precautions (5.2)]

Skin and Subcutaneous Tissue Disorders: Toxic epidermal necrolysis, Stevens-Johnson syndrome [see Warnings and Precautions (5.2)]

Nervous System Disorders: Headache

Vascular Disorders: Hypertension

Gastrointestinal Disorders: Abdominal pain, nausea, vomiting

General Disorders and Administration Site Conditions: Malaise

7 DRUG INTERACTIONS

7.1 Potential for PAXLOVID to Affect Other Drugs

PAXLOVID (nirmatrelvir co-packaged with ritonavir) is a strong inhibitor of CYP3A, and an inhibitor of CYP2D6, P-gp and OATP1B1. Co-administration of PAXLOVID with drugs that are primarily metabolized by CYP3A and CYP2D6 or are transported by P-gp or OATP1B1 may result in increased plasma concentrations of such drugs and increase the risk of adverse events. Co-administration of PAXLOVID with drugs highly dependent on CYP3A for clearance and for which elevated plasma concentrations are associated with serious and/or life-threatening events is contraindicated [see Contraindications (4) and Drug Interactions (7.3) Table 2]. Co-administration with other CYP3A substrates may require a dose adjustment or additional monitoring as shown in Table 2.

7.2 Potential for Other Drugs to Affect PAXLOVID

Nirmatrelvir and ritonavir are CYP3A substrates; therefore, drugs that induce CYP3A may decrease nirmatrelvir and ritonavir plasma concentrations and reduce PAXLOVID therapeutic effect [see Contraindications (4) and Drug Interactions (7.3) Table 2].

7.3 Established and Other Potentially Significant Drug Interactions

Table 2 provides a listing of clinically significant drug interactions, including contraindicated drugs [see Contraindications (4) and Warnings and Precautions (5.1)]. Drugs listed in Table 2 are a guide and not considered a comprehensive list of all possible drugs that may interact with PAXLOVID. The healthcare provider should consult other appropriate resources such as the prescribing information for the interacting drug for comprehensive information on dosing or monitoring with concomitant use of a strong CYP3A inhibitor such as ritonavir.

Table 2: Established and Other Potentially Significant Drug Interactions
Drug Class | Drugs within Class | Effect on Concentration | Clinical Comments
Alpha 1- adrenoreceptor antagonist | alfuzosin | ↑ alfuzosin | Co-administration contraindicated due to potential hypotension [see Contraindications (4)].
Alpha 1- adrenoreceptor antagonist | tamsulosin | ↑ tamsulosin | Avoid concomitant use with PAXLOVID.
Antianginal | ranolazine | ↑ ranolazine | Co-administration contraindicated due to potential for serious and/or life-threatening reactions [see Contraindications (4)].
Antiarrhythmics | amiodarone, dronedarone, flecainide, propafenone, quinidine | ↑ antiarrhythmic | Co-administration contraindicated due to potential for cardiac arrhythmias [see Contraindications (4)].
Antiarrhythmics | lidocaine (systemic), disopyramide | ↑ antiarrhythmic | Caution is warranted and therapeutic concentration monitoring is recommended for antiarrhythmics if available.
Anticancer drugs | apalutamide,; enzalutamide | ↓ nirmatrelvir/ritonavir | Co-administration contraindicated due to potential loss of virologic response and possible resistance [see Contraindications (4)].
Anticancer drugs | abemaciclib, ceritinib, dasatinib, encorafenib, ibrutinib, ivosidenib, neratinib, nilotinib, venetoclax, vinblastine, vincristine | ↑ anticancer drugs | Avoid co-administration of encorafenib or ivosidenib due to potential risk of serious adverse events such as QT interval prolongation. Avoid use of neratinib, venetoclax or ibrutinib. Co-administration of vincristine and vinblastine may lead to significant hematologic or gastrointestinal side effects. For further information, refer to the individual product prescribing information for anticancer drug.
Anticoagulants | warfarin | ↑↓ warfarin | Closely monitor international normalized ratio (INR) if co-administration with warfarin is necessary.
 | rivaroxaban | ↑ rivaroxaban | Increased bleeding risk with rivaroxaban. Avoid concomitant use.
 | dabigatran [See Pharmacokinetics, Clinical Drug Interaction Studies (12.3).] | ↑ dabigatran | Increased bleeding risk with dabigatran. Depending on dabigatran indication and renal function, reduce dose of dabigatran or avoid concomitant use. Refer to the dabigatran prescribing information for further information.
 | apixaban | ↑ apixaban | Combined P-gp and strong CYP3A inhibitors increase blood levels of apixaban and increase the risk of bleeding. Dosing recommendations for co-administration of apixaban with PAXLOVID depend on the apixaban dose. Refer to the apixaban prescribing information for more information.
Anticonvulsants | carbamazepine, phenobarbital, primidone, phenytoin | ↓ nirmatrelvir/ritonavir | Co-administration contraindicated due to potential loss of virologic response and possible resistance [see Contraindications (4)].
Anticonvulsants | clonazepam | ↑ anticonvulsant | A dose decrease may be needed for clonazepam when co-administered with PAXLOVID and clinical monitoring is recommended.
Antidepressants | bupropion | ↓ bupropion and active metabolite hydroxy-bupropion | Monitor for an adequate clinical response to bupropion.
 | trazodone | ↑ trazodone | Adverse reactions of nausea, dizziness, hypotension, and syncope have been observed following co-administration of trazodone and ritonavir. A lower dose of trazodone should be considered. Refer to the trazadone prescribing information for further information.
Antifungals | voriconazole | ↓ voriconazole | Avoid concomitant use of voriconazole.
 | ketoconazole, isavuconazonium sulfate, itraconazole | ↑ ketoconazole ↑ isavuconazonium sulfate ↑ itraconazole | Refer to the ketoconazole, isavuconazonium sulfate, and itraconazole prescribing information for further information.
 |  | ↑ nirmatrelvir/ritonavir | A nirmatrelvir/ritonavir dose reduction is not needed.
Anti-gout | colchicine | ↑ colchicine | Co-administration contraindicated due to potential for serious and/or life-threatening reactions in patients with renal and/or hepatic impairment [see Contraindications (4)].
Anti-HIV protease inhibitors | atazanavir, darunavir, tipranavir | ↑ protease inhibitor | For further information, refer to the respective protease inhibitors' prescribing information. Patients on ritonavir- or cobicistat-containing HIV regimens should continue their treatment as indicated. Monitor for increased PAXLOVID or protease inhibitor adverse events.
Anti-HIV | efavirenz, maraviroc, nevirapine, zidovudine, bictegravir/ emtricitabine/ tenofovir | ↑ efavirenz ↑ maraviroc ↑ nevirapine ↓ zidovudine ↑ bictegravir ↔ emtricitabine ↑ tenofovir | For further information, refer to the respective anti-HIV drugs prescribing information.
Anti-infective | clarithromycin, erythromycin | ↑ clarithromycin ↑ erythromycin | Refer to the respective prescribing information for anti-infective dose adjustment.
Antimycobacterial | rifampin, rifapentine | ↓ nirmatrelvir/ritonavir | Co-administration contraindicated due to potential loss of virologic response and possible resistance. Alternate antimycobacterial drugs such as rifabutin should be considered [see Contraindications (4)].
Antimycobacterial | bedaquiline | ↑ bedaquiline | Refer to the bedaquiline prescribing information for further information.
 | rifabutin | ↑ rifabutin | Refer to the rifabutin prescribing information for further information on rifabutin dose reduction.
Antipsychotics | lurasidone, pimozide | ↑ lurasidone ↑ pimozide | Co-administration contraindicated due to serious and/or life-threatening reactions such as cardiac arrhythmias [see Contraindications (4)].
Antipsychotics | quetiapine | ↑ quetiapine | If co-administration is necessary, reduce quetiapine dose and monitor for quetiapine-associated adverse reactions. Refer to the quetiapine prescribing information for recommendations.
 | clozapine | ↑ clozapine | If co-administration is necessary, consider reducing the clozapine dose and monitor for adverse reactions.
Benign prostatic hyperplasia agents | silodosin | ↑ silodosin | Co-administration contraindicated due to potential for postural hypotension [see Contraindications (4)].
Calcium channel blockers | amlodipine, diltiazem, felodipine, nicardipine, nifedipine, verapamil | ↑ calcium channel blocker | Caution is warranted and clinical monitoring of patients is recommended. A dose decrease may be needed for these drugs when co-administered with PAXLOVID. If co-administered, refer to the individual product prescribing information for calcium channel blocker for further information.
Cardiac glycosides | digoxin | ↑ digoxin | Caution should be exercised when co-administering PAXLOVID with digoxin, with appropriate monitoring of serum digoxin levels. Refer to the digoxin prescribing information for further information.
Cardiovascular agents | eplerenone | ↑ eplerenone | Co-administration with eplerenone is contraindicated due to potential for hyperkalemia [see Contraindications (4)].
 | ivabradine | ↑ ivabradine | Co-administration with ivabradine is contraindicated due to potential for bradycardia or conduction disturbances [see Contraindications (4)].
Cardiovascular agents | aliskiren, ticagrelor, vorapaxar clopidogrel | ↑ aliskiren ↑ ticagrelor ↑ vorapaxar ↓ clopidogrel active metabolite | Avoid concomitant use with PAXLOVID.
 | cilostazol | ↑ cilostazol | Dosage adjustment of cilostazol is recommended. Refer to the cilostazol prescribing information for more information.
 | mavacamten | ↑ mavacamten | Co-administration with mavacamten may increase mavacamten plasma concentration and increase the risk of heart failure. Discontinue mavacamten for the duration of PAXLOVID treatment. Resumption of mavacamten within 5 days of completing PAXLOVID may result in higher exposure of mavacamten. Refer to the mavacamten prescribing information for more information.
Corticosteroids primarily metabolized by CYP3A | betamethasone, budesonide, ciclesonide, dexamethasone, fluticasone, methylprednisolone, mometasone, triamcinolone | ↑ corticosteroid | Co-administration with corticosteroids (all routes of administration) of which exposures are significantly increased by strong CYP3A inhibitors can increase the risk for Cushing’s syndrome and adrenal suppression. However, the risk of Cushing’s syndrome and adrenal suppression associated with short-term use of a strong CYP3A inhibitor is low. Alternative corticosteroids including beclomethasone, prednisone, and prednisolone should be considered.
Cystic fibrosis transmembrane conductance regulator potentiators | lumacaftor/ivacaftor | ↓ nirmatrelvir/ritonavir | Co-administration contraindicated due to potential loss of virologic response and possible resistance [see Contraindications (4)].
Cystic fibrosis transmembrane conductance regulator potentiators | ivacaftor elexacaftor/tezacaftor/ ivacaftor tezacaftor/ivacaftor | ↑ ivacaftor ↑ elexacaftor/tezacaftor/ ivacaftor ↑ tezacaftor/ivacaftor | Reduce dosage when co-administered with PAXLOVID. Refer to the individual product prescribing information for more information.
Dipeptidyl peptidase 4 (DPP4) inhibitors | saxagliptin | ↑ saxagliptin | Dosage adjustment of saxagliptin is recommended. Refer to the saxagliptin prescribing information for more information.
Endothelin receptor antagonists | bosentan | ↑ bosentan ↓ nirmatrelvir/ritonavir | Discontinue use of bosentan at least 36 hours prior to initiation of PAXLOVID. Refer to the bosentan prescribing information for further information.
Ergot derivatives | dihydroergotamine, ergotamine, methylergonovine | ↑ dihydroergotamine ↑ ergotamine ↑ methylergonovine | Co-administration contraindicated due to potential for acute ergot toxicity characterized by vasospasm and ischemia of the extremities and other tissues including the central nervous system [see Contraindications (4)].
Hepatitis C direct acting antivirals | elbasvir/grazoprevir | ↑ antiviral | Increased grazoprevir concentrations can result in alanine transaminase (ALT) elevations.
 | glecaprevir/pibrentasvir |  | Avoid concomitant use of glecaprevir/pibrentasvir with PAXLOVID.
 | ombitasvir/paritaprevir/ritonavir and dasabuvir |  | Refer to the ombitasvir/paritaprevir/ritonavir and dasabuvir label for further information.
 | sofosbuvir/velpatasvir/voxilaprevir |  | Refer to the sofosbuvir/velpatasvir/voxilaprevir prescribing information for further information. Patients on ritonavir-containing HCV regimens should continue their treatment as indicated. Monitor for increased PAXLOVID or HCV drug adverse events with concomitant use.
Herbal products | St. John's Wort (hypericum perforatum) | ↓ nirmatrelvir/ritonavir | Co-administration contraindicated due to potential loss of virologic response and possible resistance [see Contraindications (4)].
HMG-CoA reductase inhibitors | lovastatin, simvastatin | ↑ lovastatin ↑ simvastatin | Co-administration contraindicated due to potential for myopathy including rhabdomyolysis [see Contraindications (4)]. If treatment with PAXLOVID is considered medically necessary, discontinue use of lovastatin and simvastatin at least 12 hours prior to initiation of PAXLOVID, during the 5 days of PAXLOVID treatment, and for 5 days after completing PAXLOVID.
HMG-CoA reductase inhibitors | atorvastatin | ↑ atorvastatin | Consider temporary discontinuation of atorvastatin during treatment with PAXLOVID. Atorvastatin does not need to be withheld prior to or after completing PAXLOVID.
Hormonal contraceptive | ethinyl estradiol | ↓ ethinyl estradiol | An additional, non-hormonal method of contraception should be considered during the 5 days of PAXLOVID treatment and until one menstrual cycle after stopping PAXLOVID.
Immunosuppressants | voclosporin | ↑ voclosporin | Co-administration contraindicated due to potential for acute and/or chronic nephrotoxicity [see Contraindications (4)].
Immunosuppressants | calcineurin inhibitors: cyclosporine, tacrolimus | ↑ cyclosporine ↑ tacrolimus | Avoid concomitant use of calcineurin inhibitors with PAXLOVID when close monitoring of immunosuppressant concentrations is not feasible. If co-administered, dose adjustment of the immunosuppressant and close and regular monitoring for immunosuppressant concentrations and adverse reactions are recommended during and after treatment with PAXLOVID. Obtain expert consultation to appropriately manage the complexity of this co-administration [see Warnings and Precautions (5.1)].
 | mTOR inhibitors: everolimus, sirolimus | ↑ everolimus ↑ sirolimus | Avoid concomitant use of everolimus and sirolimus and PAXLOVID. Refer to the individual immunosuppressant prescribing information and latest guidelines for further information.
Janus kinase (JAK) inhibitors | tofacitinib | ↑ tofacitinib | Dosage adjustment of tofacitinib is recommended. Refer to the tofacitinib prescribing information for more information.
 | upadacitinib | ↑ upadacitinib | Dosing recommendations for co-administration of upadacitinib with PAXLOVID depends on the upadacitinib indication. Refer to the upadacitinib prescribing information for more information.
Long-acting beta-adrenoceptor agonist | salmeterol | ↑ salmeterol | Avoid concomitant use with PAXLOVID. The combination may result in increased risk of cardiovascular adverse events associated with salmeterol, including QT prolongation, palpitations, and sinus tachycardia.
Microsomal triglyceride transfer protein (MTTP) inhibitor | lomitapide | ↑ lomitapide | Co-administration contraindicated due to potential for hepatotoxicity and gastrointestinal adverse reactions [see Contraindications (4)].
Migraine medications | eletriptan | ↑ eletriptan | Co-administration of eletriptan within at least 72 hours of PAXLOVID is contraindicated due to potential for serious adverse reactions including cardiovascular and cerebrovascular events [see Contraindications (4)].
 | ubrogepant | ↑ ubrogepant | Co-administration of ubrogepant with PAXLOVID is contraindicated due to potential for serious adverse reactions [see Contraindications (4)].
Migraine medications | rimegepant | ↑ rimegepant | Avoid concomitant use with PAXLOVID.
Mineralocorticoid receptor antagonists | finerenone | ↑ finerenone | Co-administration contraindicated due to potential for serious adverse reactions including hyperkalemia, hypotension, and hyponatremia [see Contraindications (4)].
Muscarinic receptor antagonists | darifenacin | ↑ darifenacin | The darifenacin daily-dose should not exceed 7.5 mg when co-administered with PAXLOVID. Refer to the darifenacin prescribing information for more information.
Narcotic analgesics | fentanyl, hydrocodone, oxycodone, meperidine | ↑ fentanyl ↑ hydrocodone ↑ oxycodone ↑ meperidine | Careful monitoring of therapeutic and adverse effects (including potentially fatal respiratory depression) is recommended when fentanyl, hydrocodone, oxycodone, or meperidine is concomitantly administered with PAXLOVID. If concomitant use with PAXLOVID is necessary, consider a dosage reduction of the narcotic analgesic and monitor patients closely at frequent intervals. Refer to the individual product prescribing information for more information.
 | methadone | ↓ methadone | Monitor methadone-maintained patients closely for evidence of withdrawal effects and adjust the methadone dose accordingly.
Neuropsychiatric agents | suvorexant | ↑ suvorexant | Avoid concomitant use of suvorexant with PAXLOVID.
 | aripiprazole, brexpiprazole, cariprazine, iloperidone, lumateperone, pimavanserin | ↑ aripiprazole ↑ brexpiprazole ↑ cariprazine ↑ iloperidone ↑ lumateperone ↑ pimavanserin | Dosage adjustment of aripiprazole, brexpiprazole, cariprazine, iloperidone, lumateperone, and pimavanserin is recommended. Refer to the individual product prescribing information for more information.
Non-opioid analgesic (selective blocker of Nav1.8 sodium channels) | suzetrigine | ↑ suzetrigine and active metabolite M6‑SUZ | Co-administration contraindicated due to potential for serious and/or life-threatening suzetrigine adverse reactions [see Contraindications (4)].
Opioid antagonists | naloxegol | ↑ naloxegol | Co-administration contraindicated due to the potential for opioid withdrawal symptoms [see Contraindications (4)].
Pulmonary hypertension agents (PDE5 inhibitors) | sildenafil (Revatio®) | ↑ sildenafil | Co-administration of sildenafil with PAXLOVID is contraindicated for use in pulmonary hypertension due to the potential for sildenafil associated adverse events, including visual abnormalities hypotension, prolonged erection, and syncope [see Contraindications (4)].
Pulmonary hypertension agents (PDE5 inhibitors) | tadalafil (Adcirca®) | ↑ tadalafil | Avoid concomitant use of tadalafil with PAXLOVID for pulmonary hypertension.
Pulmonary hypertension agents (sGC stimulators) | riociguat | ↑ riociguat | Dosage adjustment is recommended for riociguat when used for pulmonary hypertension. Refer to the riociguat prescribing information for more information.
Erectile dysfunction agents (PDE5 inhibitors) | avanafil | ↑ avanafil | Do not use PAXLOVID with avanafil because a safe and effective avanafil dosage regimen has not been established.
 | sildenafil, tadalafil, vardenafil | ↑ sildenafil ↑ tadalafil ↑ vardenafil | Dosage adjustment is recommended for use of sildenafil, tadalafil or vardenafil with PAXLOVID when used for erectile dysfunction. Refer to the individual product prescribing information for more information.
Sedative/hypnotics | triazolam, oral midazolam | ↑ triazolam ↑ midazolam | Co-administration contraindicated due to potential for extreme sedation and respiratory depression [see Contraindications (4)].
Sedative/hypnotics | buspirone, clorazepate, diazepam, estazolam, flurazepam, zolpidem | ↑ sedative/hypnotic | A dose decrease may be needed for these drugs when co-administered with PAXLOVID and monitoring for adverse events.
 | midazolam (administered parenterally) | ↑ midazolam | Co-administration of midazolam (parenteral) should be done in a setting which ensures close clinical monitoring and appropriate medical management in case of respiratory depression and/or prolonged sedation. Dosage reduction for midazolam should be considered, especially if more than a single dose of midazolam is administered. Refer to the midazolam prescribing information for further information.
Serotonin receptor 1A agonist/ serotonin receptor 2A antagonist | flibanserin | ↑ flibanserin | Co-administration contraindicated due to potential for hypotension, syncope, and CNS depression [see Contraindications (4)].
Vasopressin receptor antagonists | tolvaptan | ↑ tolvaptan | Co-administration contraindicated due to potential for dehydration, hypovolemia and hyperkalemia [see Contraindications (4)].

8 USE IN SPECIFIC POPULATIONS

8.1 Pregnancy

Risk Summary

Available data on the use of nirmatrelvir during pregnancy are insufficient to evaluate for a drug-associated risk of major birth defects, miscarriage, or adverse maternal or fetal outcomes. Published observational studies on ritonavir use in pregnant women have not identified an increase in the risk of major birth defects. Published studies with ritonavir are insufficient to identify a drug associated risk of miscarriage (see Data). There are maternal and fetal risks associated with untreated COVID-19 in pregnancy (see Clinical Considerations).

In an embryo-fetal development study with nirmatrelvir, reduced fetal body weights following oral administration of nirmatrelvir to pregnant rabbits were observed at systemic exposures (AUC) approximately 11 times higher than clinical exposure at the approved human dose of PAXLOVID. No other adverse developmental outcomes were observed in animal reproduction studies with nirmatrelvir at systemic exposures (AUC) greater than or equal to 3 times higher than clinical exposure at the approved human dose of PAXLOVID (see Data).

In embryo-fetal developmental studies with ritonavir, no evidence of adverse developmental outcomes was observed following oral administration of ritonavir to pregnant rats and rabbits at systemic exposures (AUC) 5 (rat) or 8 (rabbits) times higher than clinical exposure at the approved human dose of PAXLOVID (see Data).

The estimated background risk of major birth defects and miscarriage for the indicated population is unknown. All pregnancies have a risk of birth defect, loss, or other adverse outcomes. In the U.S. general population, the estimated background risk of major birth defects and miscarriage in clinically recognized pregnancies is 2% to 4% and 15% to 20%, respectively.

Clinical Considerations

Disease-associated Maternal and/or Embryo-fetal Risk

COVID-19 in pregnancy is associated with adverse maternal and fetal outcomes, including preeclampsia, eclampsia, preterm birth, premature rupture of membranes, venous thromboembolic disease, and fetal death.

Data

Human Data

Ritonavir

Based on prospective reports to the antiretroviral pregnancy registry of live births following exposure to ritonavir-containing regimens (including over 3,500 live births exposed in the first-trimester and over 3,500 live births exposed in the second and third trimesters), there was no difference in the rate of overall birth defects for ritonavir compared with the background birth defect rate of 2.7% in the U.S. reference population of the Metropolitan Atlanta Congenital Defects Program (MACDP). The prevalence of birth defects in live births was 2.4% [95% confidence interval (CI): 1.9%, 2.9%] following first-trimester exposure to ritonavir-containing regimens and 2.9% (95% CI: 2.4%, 3.5%) following second and third trimester exposure to ritonavir-containing regimens. While placental transfer of ritonavir and fetal ritonavir concentrations are generally low, detectable levels have been observed in cord blood samples and neonate hair.

Animal Data

Nirmatrelvir

Embryo-fetal developmental (EFD) toxicity studies were conducted in pregnant rats and rabbits administered oral nirmatrelvir doses of up to 1,000 mg/kg/day during organogenesis [on Gestation Days (GD) 6 through 17 in rats and GD 7 through 19 in rabbits]. No biologically significant developmental effects were observed in the rat EFD study. At the highest dose of 1,000 mg/kg/day, the systemic nirmatrelvir exposure (AUC24) in rats was approximately 9 times higher than clinical exposures at the approved human dose of PAXLOVID. In the rabbit EFD study, lower fetal body weights (9% decrease) were observed at 1,000 mg/kg/day in the absence of significant maternal toxicity findings. At 1,000 mg/kg/day, the systemic exposure (AUC24) in rabbits was approximately 11 times higher than clinical exposures at the approved human dose of PAXLOVID. No other significant developmental toxicities (malformations and embryo-fetal lethality) were observed up to the highest dose tested, 1,000 mg/kg/day. No developmental effects were observed in rabbits at 300 mg/kg/day resulting in systemic exposure (AUC24) approximately 3 times higher than clinical exposures at the approved human dose of PAXLOVID. A pre- and postnatal developmental (PPND) study in pregnant rats administered oral nirmatrelvir doses of up to 1,000 mg/kg/day from GD 6 through Lactation Day (LD) 20 showed no adverse findings. Although no difference in body weight was noted at birth when comparing offspring born to nirmatrelvir-treated versus control animals, a decrease in the body weight of offspring was observed on Postnatal Day (PND) 17 (8% decrease) and PND 21 (up to 7% decrease) in the absence of maternal toxicity. No significant differences in offspring body weight were observed from PND 28 to PND 56. The maternal systemic exposure (AUC24) at 1,000 mg/kg/day was approximately 9 times higher than clinical exposures at the approved human dose of PAXLOVID. No body weight changes in the offspring were noted at 300 mg/kg/day, where maternal systemic exposure (AUC24) was approximately 6 times higher than clinical exposures at the approved human dose of PAXLOVID.

Ritonavir

Ritonavir was administered orally to pregnant rats (at 0, 15, 35, and 75 mg/kg/day) and rabbits (at 0, 25, 50, and 110 mg/kg/day) during organogenesis (on GD 6 through 17 in rats and GD 6 through 19 in rabbits). No evidence of teratogenicity due to ritonavir was observed in rats and rabbits at systemic exposures (AUC) 5 (rats) or 8 (rabbits) times higher than exposure at the approved human dose of PAXLOVID. Increased incidences of early resorptions, ossification delays, and developmental variations, as well as decreased fetal body weights were observed in rats in the presence of maternal toxicity, at systemic exposures (AUC) approximately 10 times higher than exposure at the approved human dose of PAXLOVID. In rabbits, resorptions, decreased litter size, and decreased fetal weights were observed at maternally toxic doses, at systemic exposures greater than 8 times higher than exposure at the approved human dose of PAXLOVID. In a PPND study in rats, administration of 0, 15, 35, and 60 mg/kg/day ritonavir from GD 6 through PND 20 resulted in no developmental toxicity, at ritonavir systemic exposures greater than 10 times the exposure at the approved human dose of PAXLOVID.

8.2 Lactation

Risk Summary

Nirmatrelvir and ritonavir are present in human breast milk in small amounts (less than 2%). In a clinical lactation study in 8 lactating women, nirmatrelvir and ritonavir were estimated to be present in human milk at a mean weight-normalized infant daily dose of 0.16 mg/kg/day (1.8% of maternal weight-adjusted daily dose) and 0.006 mg/kg/day (0.2% of maternal weight-adjusted daily dose), respectively (see Data).

There are no available data on the effects of nirmatrelvir or ritonavir on the breastfed infant or on milk production. The developmental and health benefits of breastfeeding should be considered along with the mother's clinical need for PAXLOVID and any potential adverse effects on the breastfed infant from PAXLOVID or from the underlying maternal condition. Breastfeeding individuals with COVID-19 should follow practices according to clinical guidelines to avoid exposing the infant to COVID-19.

Data

In a clinical pharmacokinetics study, 8 healthy lactating women who were at least 12 weeks postpartum were administered 3 oral doses every 12 hours (steady state dosing) of 300 mg/100 mg nirmatrelvir/ritonavir. The mean daily amount of nirmatrelvir and ritonavir recovered in breast milk was 0.752 mg and 0.027 mg, respectively, representing 0.13% and 0.014% of the corresponding administered daily maternal doses (unadjusted for weight). The estimated daily infant dose (assuming average milk consumption of 150 mL/kg/day), was 0.16 mg/kg/day and 0.006 mg/kg/day, 1.8% and 0.2% of the maternal dose, respectively, for nirmatrelvir and ritonavir.

8.3 Females and Males of Reproductive Potential

Contraception

Use of ritonavir may reduce the efficacy of combined hormonal contraceptives. Advise patients using combined hormonal contraceptives to use an effective alternative contraceptive method or an additional barrier method of contraception [see Drug Interactions (7.3)].

8.4 Pediatric Use

The optimal dose of PAXLOVID has not been established in pediatric patients.

8.5 Geriatric Use

Clinical studies of PAXLOVID include subjects 65 years of age and older and their data contributes to the overall assessment of safety and efficacy [see Adverse Reactions (6.1) and Clinical Studies (14.1)]. Of the total number of subjects in the integrated dataset consisting of EPIC-HR and EPIC-SR who were randomized to and received PAXLOVID (N=1,578), 165 (10%) were 65 years of age and older and 39 (2%) were 75 years of age and older. No overall differences in safety were observed between these subjects and younger subjects, and other reported clinical experience has not identified differences in safety between the elderly and younger patients, but greater sensitivity of some older individuals cannot be ruled out.

8.6 Renal Impairment

Renal impairment increases nirmatrelvir exposure, which may increase the risk of PAXLOVID adverse reactions. No dosage adjustment is recommended in patients with mild renal impairment (eGFR ≥60 to <90 mL/min). Reduce the PAXLOVID dosage in patients with moderate renal impairment (eGFR ≥30 to <60 mL/min). Reduce the PAXLOVID dose and dose frequency in patients with severe renal impairment (eGFR <30 mL/min), including those requiring hemodialysis. On days when patients undergo hemodialysis, the PAXLOVID dose should be administered after hemodialysis [see Dosage and Administration (2.3), Adverse Reactions (6.1), and Clinical Pharmacology (12.3)]. Prescriptions should specify the numeric dose of each active ingredient within PAXLOVID. Providers should counsel patients about renal dosing instructions [see Patient Counseling Information (17)].

8.7 Hepatic Impairment

No dosage adjustment of PAXLOVID is recommended for patients with mild (Child-Pugh Class A) or moderate (Child-Pugh Class B) hepatic impairment. No pharmacokinetic or safety data are available regarding the use of nirmatrelvir or ritonavir in subjects with severe (Child-Pugh Class C) hepatic impairment, therefore, PAXLOVID is not recommended for use in patients with severe (Child-Pugh Class C) hepatic impairment [see Warnings and Precautions (5.3) and Clinical Pharmacology (12.3)].

10 OVERDOSAGE

Treatment of overdose with PAXLOVID should consist of general supportive measures including monitoring of vital signs and observation of the clinical status of the patient. There is no specific antidote for overdose with PAXLOVID.

11 DESCRIPTION

PAXLOVID is nirmatrelvir tablets co-packaged with ritonavir tablets. Nirmatrelvir is a SARS-CoV-2 main protease (Mpro) inhibitor, and ritonavir is an HIV-1 protease inhibitor and CYP3A inhibitor.

Nirmatrelvir

The chemical name of active ingredient of nirmatrelvir is (1R,2S,5S)-N-((1S)-1-Cyano-2-((3S)-2-oxopyrrolidin-3-yl)ethyl)-3-((2S)-3,3-dimethyl-2-(2,2,2-trifluoroacetamido)butanoyl)-6,6-dimethyl-3-azabicyclo[3.1.0]hexane-2-carboxamide]. It has a molecular formula of C23H32F3N5O4 and a molecular weight of 499.54. Nirmatrelvir has the following structural formula:

Nirmatrelvir is available as immediate-release, film-coated tablets. Each tablet contains 150 mg nirmatrelvir with the following inactive ingredients: colloidal silicon dioxide, croscarmellose sodium, lactose monohydrate, microcrystalline cellulose, and sodium stearyl fumarate. The following are the ingredients in the film coating: hydroxy propyl methylcellulose, iron oxide red, polyethylene glycol, and titanium dioxide.

Ritonavir

Ritonavir is chemically designated as 10-Hydroxy-2-methyl-5-(1-methylethyl)-1- [2-(1 methylethyl)-4-thiazolyl]-3,6-dioxo-8,11-bis(phenylmethyl)-2,4,7,12- tetraazatridecan-13-oic acid, 5-thiazolylmethyl ester, [5S-(5R*,8R*,10R*,11R*)]. Its molecular formula is C37H48N6O5S2, and its molecular weight is 720.95. Ritonavir has the following structural formula:

Ritonavir is available as film-coated tablets. Each tablet contains 100 mg ritonavir with the following inactive ingredients: anhydrous dibasic calcium phosphate, colloidal silicon dioxide, copovidone, sodium stearyl fumarate, and sorbitan monolaurate. The film coating may include the following ingredients: colloidal anhydrous silica, colloidal silicon dioxide, hydroxypropyl cellulose, hypromellose, polyethylene glycol, polysorbate 80, talc, and titanium dioxide.

12 CLINICAL PHARMACOLOGY

12.1 Mechanism of Action

Nirmatrelvir is a severe acute respiratory syndrome coronavirus 2 (SARS-CoV-2) antiviral drug [see Microbiology (12.4)].

Ritonavir is an HIV-1 protease inhibitor but is not active against SARS-CoV-2 Mpro. Ritonavir inhibits the CYP3A-mediated metabolism of nirmatrelvir, resulting in increased plasma concentrations of nirmatrelvir.

12.2 Pharmacodynamics

Cardiac Electrophysiology

At 3 times the steady state peak plasma concentration (Cmax) at the recommended dose, nirmatrelvir does not prolong the QTc interval to any clinically relevant extent.

12.3 Pharmacokinetics

The pharmacokinetics of nirmatrelvir/ritonavir were similar in healthy subjects and in subjects with mild-to-moderate COVID-19.

Nirmatrelvir AUC increased in a less than dose proportional manner over a single dose range from 250 mg to 750 mg (0.83 to 2.5 times the approved recommended dose) and multiple dose range from 75 mg to 500 mg (0.25 to 1.67 times the approved recommended dose), when administered in combination with 100 mg ritonavir. Nirmatrelvir steady state was achieved on Day 2 following administration of the approved recommended dosage and the mean accumulation ratio was approximately 2-fold.

The pharmacokinetic properties of nirmatrelvir/ritonavir are displayed in Table 3.

Table 3: Pharmacokinetic Properties of Nirmatrelvir and Ritonavir in Healthy Subjects
 | Nirmatrelvir (When Given With Ritonavir) | Ritonavir
Absorption
Tmax (hr), median | 3.00 [Represents data after a single dose of 300 mg nirmatrelvir (2 × 150 mg tablet formulation) administered together with 100 mg ritonavir tablet in healthy subjects.] | 3.98
Food effect | Test/reference (fed/fasted) ratios of adjusted geometric means (90% CI) AUCinf and Cmax for nirmatrelvir were 119.67 (108.75, 131.68) and 161.01 (139.05, 186.44), respectively. [Following a single oral dose of nirmatrelvir 300 mg boosted ritonavir 100 mg at -12 hours, 0 hours and 12 hours, administered under fed (high fat and high calorie meal) or fasted conditions.]
Distribution
% bound to human plasma proteins | 69% | 98–99%
Blood-to-plasma ratio | 0.60 | 0.14 [Red blood cell to plasma ratio.]
Vz/F (L), mean | 104.7 [300 mg nirmatrelvir (oral suspension formulation) co-administered with 100 mg ritonavir (tablet formulation) twice daily for 3 days.] | 112.4
Elimination
Major route of elimination | Renal elimination | Hepatic metabolism
Half-life (T½) (hr), mean | 6.05 | 6.15
Oral clearance (CL/F) (L/hr), mean | 8.99 | 13.92
Metabolism
Metabolic pathways | Nirmatrelvir is a CYP3A substrate but when dosed with ritonavir, metabolic clearance is minimal. | Major CYP3A, Minor CYP2D6
Excretion
% drug-related material in feces | 35.3% [Determined by ^19F-NMR analysis following 300 mg nirmatrelvir oral suspension administered at 0 hr enhanced with 100 mg ritonavir at -12 hours, 0 hours, 12 hours, and 24 hours.] | 86.4% [Determined by ^14C analysis following 600 mg ^14C-ritonavir oral solution (6 times the approved ritonavir dose).]
% of dose excreted as total (unchanged drug) in feces | 27.5% | 33.8%
% drug-related material in urine | 49.6% | 11.3%
% of dose excreted as total (unchanged drug) in urine | 55.0% | 3.5%
Abbreviations: CL/F=apparent clearance; hr=hour; L/hr=liters per hour; T½=terminal elimination half-life; Tmax=the time to reach Cmax; Vz/F=apparent volume of distribution.

The predicted Day 5 nirmatrelvir exposure parameters in adult subjects with mild-to-moderate COVID-19 who were treated with PAXLOVID in EPIC-HR are presented in Table 4.

Table 4: Predicted Day 5 Nirmatrelvir Exposure Parameters Following Administration of Nirmatrelvir/Ritonavir 300 mg/100 mg Twice Daily in Subjects with Mild-to-Moderate COVID-19
Pharmacokinetic Parameter (units) [Data presented as geometric mean (10th and 90th percentile).] | Nirmatrelvir [Based on 1,017 subjects with their post hoc PK parameters.]
Cmax (µg/mL) | 3.29 (1.93, 5.40)
AUCtau (µg*hr/mL) [AUCtau=predicted area under the plasma concentration-time profile from time 0 to 12 hours for twice-daily dosing.] | 28.3 (12.5, 52.5)
Cmin (µg/mL) | 1.40 (0.48, 3.45)
Abbreviations: Cmax=predicted maximal concentration; Cmin=predicted minimal concentration (Ctrough).

Effect of Food

No clinically significant differences in the pharmacokinetics of nirmatrelvir were observed following administration of a high fat meal (800-1,000 calories; 50% fat) to healthy subjects.

Specific Populations

There were no clinically significant differences in the pharmacokinetics of nirmatrelvir based on age (18 to 86 years), sex, or race/ethnicity.

Pediatric Patients

The pharmacokinetics of nirmatrelvir/ritonavir in patients less than 18 years of age have not been established.

Patients with Renal Impairment

The pharmacokinetics of nirmatrelvir in subjects with renal impairment following administration of a single oral dose of nirmatrelvir 100 mg (0.33 times the approved recommended dose) co-administered with ritonavir 100 mg were determined. Compared to healthy controls with no renal impairment, the Cmax and AUC of nirmatrelvir in subjects with mild renal impairment was 30% and 24% higher, in subjects with moderate renal impairment was 38% and 87% higher, and in subjects with severe renal impairment was 48% and 204% higher, respectively.

The pharmacokinetics of nirmatrelvir in subjects with mild-to-moderate COVID-19 and severe renal impairment (eGFR<30 mL/min) either requiring intermittent hemodialysis (n=12) or not requiring hemodialysis (n=2) were evaluated after administration of 300 mg/100 mg nirmatrelvir/ritonavir once on Day 1 followed by 150 mg/100 mg nirmatrelvir/ritonavir once daily on Days 2-5 for a total of 5 doses.

The administration of 300 mg/100 mg nirmatrelvir/ritonavir once on Day 1 followed by 150 mg/100 mg nirmatrelvir/ritonavir once daily on Days 2-5 in subjects with severe renal impairment, either requiring intermittent hemodialysis or not requiring hemodialysis resulted in comparable exposures on Day 1 and at steady-state (AUC0-24 and Cmax) compared to those observed in subjects with normal renal function receiving 300 mg/100 mg nirmatrelvir/ritonavir twice daily for 5 days. During a 4-hour hemodialysis session, approximately 6.9% of nirmatrelvir dose was cleared through dialysis. Hemodialysis clearance was 1.83 L/h.

Patients with Hepatic Impairment

The pharmacokinetics of nirmatrelvir were similar in patients with moderate (Child-Pugh Class B) hepatic impairment compared to healthy subjects following administration of a single oral dose of nirmatrelvir 100 mg (0.33 times the approved recommended dose) co-administered with ritonavir 100 mg. The impact of severe hepatic impairment (Child-Pugh Class C) on the pharmacokinetics of nirmatrelvir or ritonavir has not been studied.

Clinical Drug Interaction Studies

Table 5 describes the effect of other drugs on the Cmax and AUC of nirmatrelvir.

Table 5: The Effect of Other Drugs on the Pharmacokinetic Parameters of Nirmatrelvir
Co-administered Drug | Dose (Schedule) |  | N | Percent Ratio (in combination with co-administered drug/alone) of Nirmatrelvir Pharmacokinetic Parameters (90% CI); No Effect=100
Co-administered Drug | Co-administered Drug | Nirmatrelvir/ Ritonavir | N | Cmax | AUC [For carbamazepine, AUC=AUCinf; for itraconazole, AUC=AUCtau.]
Carbamazepine [Carbamazepine titrated up to 300 mg twice daily on Day 8 through Day 15 (e.g., 100 mg twice daily on Day 1 through Day 3 and 200 mg twice daily on Day 4 through Day 7).] | 300 mg twice daily (16 doses) | 300 mg/100 mg once daily (2 doses) | 10 | 56.82 (47.04, 68.62) | 44.50 (33.77, 58.65)
Itraconazole | 200 mg once daily (8 doses) | 300 mg/100 mg twice daily (5 doses) | 11 | 118.57 (112.50, 124.97) | 138.82 (129.25, 149.11)
Abbreviations: AUC=area under the plasma concentration-time curve; AUCinf=area under the plasma concentration-time profile from time zero extrapolated to infinite time; AUCtau=area under the plasma concentration-time profile from time zero to time tau (τ), the dosing interval. CI=confidence interval; Cmax=observed maximum plasma concentrations.

Table 6 describes the effect of nirmatrelvir/ritonavir on the Cmax and AUCinf of other drugs.

Table 6: Effect of Nirmatrelvir/Ritonavir on Pharmacokinetics of Other Drugs
Co-administered Drug | Dose (Schedule) |  | N | Percent Ratio of Test/Reference of Geometric Means (90% CI); No Effect=100
Co-administered Drug | Co-administered Drug | Nirmatrelvir/ Ritonavir | N | Cmax | AUCinf
Midazolam [For midazolam, Test=nirmatrelvir/ritonavir plus midazolam, Reference=Midazolam. Midazolam is an index substrate for CYP3A4. For dabigatran, Test=nirmatrelvir/ritonavir plus dabigatran, Reference=Dabigatran. Dabigatran is an index substrate for P-gp. For rosuvastatin, Test=nirmatrelvir/ritonavir plus rosuvastatin, Reference=Rosuvastatin. Rosuvastatin is an index substrate for OATP1B1.] | 2 mg (1 dose) | 300 mg/100 mg twice daily (9 doses) | 10 | 368.33 (318.91, 425.41) | 1430.02 (1204.54, 1697.71)
Dabigatran | 75 mg (1 dose) | 300 mg/100 mg twice daily (4 doses) | 24 | 233.06 (172.14, 315.54) | 194.47 (155.29, 243.55)
Rosuvastatin | 10 mg; (1 dose) | 300 mg/100 mg twice daily (3 doses) | 12 | 212.44; (174.31, 258.90) | 131.18; (115.89, 148.48)
Abbreviations: AUCinf=area under the plasma concentration-time curve from time zero extrapolated to infinite time; CI=confidence interval; Cmax=observed maximum plasma concentrations; CYP3A4=cytochrome P450 3A4; OATP1B1=organic anion transporter polypeptide 1B1; P-gp=p-glycoprotein.

In Vitro Studies

Cytochrome P450 (CYP) Enzymes:

- Nirmatrelvir is a reversible and time-dependent inhibitor of CYP3A, but not an inhibitor CYP1A2, CYP2B6, CYP2C8, CYP2C9, CYP2C19, or CYP2D6. Nirmatrelvir is an inducer of CYP2B6, 2C8, 2C9, and 3A4, but there is minimal risk for pharmacokinetic interactions arising from induction of these CYP enzymes at the proposed therapeutic dose.
- Ritonavir is a substrate of CYP2D6 and CYP3A. Ritonavir is an inducer of CYP1A2, CYP2C9, CYP2C19, CYP2B6, and CYP3A.

Transporter Systems: Nirmatrelvir is an inhibitor of P-gp and OATP1B1. Nirmatrelvir is a substrate for P-gp, but not BCRP, MATE1, MATE2K, NTCP, OAT1, OAT2, OAT3, OCT1, OCT2, PEPT1, OATP1B1, OATP1B3, OATP2B1, or OATP4C1.

12.4 Microbiology

Mechanism of Action

Nirmatrelvir is a peptidomimetic inhibitor of the SARS-CoV-2 main protease (Mpro), also referred to as 3C-like protease (3CLpro) or nonstructural protein 5 (nsp5) protease. Inhibition of SARS-CoV-2 Mpro renders it incapable of processing the viral polyproteins pp1a and pp1ab, preventing viral replication. Nirmatrelvir inhibited the activity of recombinant SARS-CoV-2 Mpro in a biochemical assay with a Ki value of 3.1 nM and an IC50 value of 19.2 nM. Nirmatrelvir was found to bind directly to the SARS-CoV-2 Mpro active site by X-ray crystallography.

Antiviral Activity

Cell Culture Antiviral Activity

Nirmatrelvir exhibited antiviral activity against SARS-CoV-2 (USA-WA1/2020 isolate) infection of differentiated normal human bronchial epithelial (dNHBE) cells with EC50 and EC90 values of 62 nM (31 ng/mL) and 181 nM (90 ng/mL), respectively, after 3 days of drug exposure.

The antiviral activity of nirmatrelvir against the Omicron sub-variants BA.2, BA.2.12.1, BA.4, BA.4.6, BA.5, BF.7, BQ.1, BQ.1.11, XBB.1.5, EG.5, and JN.1 was assessed in Vero E6-TMPRSS2 cells in the presence of a P-gp inhibitor. Nirmatrelvir had a median EC50 value of 88 nM (range: 39-146 nM) against the Omicron sub-variants, reflecting EC50 value fold changes ≤1.8 relative to the USA-WA1/2020 isolate.

In addition, the antiviral activity of nirmatrelvir against the SARS-CoV-2 Alpha, Beta, Gamma, Delta, Lambda, Mu, and Omicron BA.1 variants was assessed in Vero E6 P-gp knockout cells. Nirmatrelvir had a median EC50 value of 25 nM (range: 16-141 nM). The Beta variant was the least susceptible variant tested, with an EC50 value fold change of 3.7 relative to USA-WA1/2020. The other variants had EC50 value fold changes ≤1.1 relative to USA-WA1/2020.

Clinical Antiviral Activity

In clinical trial EPIC-HR, which enrolled subjects who were primarily infected with the SARS-CoV-2 Delta variant, PAXLOVID treatment was associated with a 0.83 log10 copies/mL greater median decline in viral RNA shedding levels in nasopharyngeal samples through Day 5 (mITT1 analysis set, all treated subjects with onset of symptoms ≤5 days who at baseline did not receive nor were expected to receive COVID-19 therapeutic mAb treatment); similar results were observed in the mITT2 analysis set (all treated subjects with onset of symptoms ≤5 days). In the EPIC-SR trial, which included subjects who were infected with SARS-CoV-2 Delta (79%) or Omicron (19%) variants, PAXLOVID treatment was associated with a 1.05 log10 copies/mL greater median decline in viral RNA shedding levels in nasopharyngeal samples through Day 5, with similar declines observed in subjects infected with Delta or Omicron variants. The degree of reduction in viral RNA levels relative to placebo following 5 days of PAXLOVID treatment was similar between unvaccinated high-risk subjects in EPIC-HR and vaccinated high-risk subjects in EPIC-SR.

Antiviral Resistance

In Cell Culture and Biochemical Assays

SARS-CoV-2 Mpro residues potentially associated with nirmatrelvir resistance have been identified using a variety of methods, including SARS-CoV-2 resistance selection, testing of recombinant SARS-CoV-2 viruses with Mpro substitutions, and biochemical assays with recombinant SARS-CoV-2 Mpro containing amino acid substitutions. Table 7 indicates Mpro substitutions and combinations of Mpro substitutions that have been observed in SARS-CoV-2 under nirmatrelvir selective pressure in cell culture. Individual Mpro substitutions are listed regardless of whether they occurred alone or in combination with other Mpro substitutions. Note that the Mpro S301P and T304I substitutions overlap the P6 and P3 positions of the nsp5/nsp6 cleavage site located at the C-terminus of Mpro. Substitutions at other Mpro cleavage sites have not been associated with nirmatrelvir resistance in cell culture. The clinical significance of these substitutions is unknown.

Table 7: SARS-CoV-2 Mpro Amino Acid Substitutions Selected by Nirmatrelvir in Cell Culture [EC50 value fold change ranges are shown in instances where multiple data points have been reported.]
Single Substitutions; (EC50 value fold change in cell culture) | T21I (1.1-4.8), S46F (ND), L50F (1.2-4.2), P108S (ND), T135I (ND), F140L (4.1), S144A (2.2-5.3), C160F (2.1), E166A (3.3), E166V (25‑288), L167F (1.9-2.5), T169I (ND), H172Y (15), A173V (0.9-2.3), V186A (ND), R188G (ND), A191V (0.7-1.5), A193P (ND), P252L (5.9), S301P (ND), and T304I (1.4-5.5).
≥2 Substitutions; (EC50 value fold change in cell culture) | T21I+S144A (9.4), T21I+E166V (83-250), T21I+A173V (3.1-8.9), T21I+T304I (3.0-7.9), L50F+E166V (34-175), L50F+T304I (5.9), T135I+T304I (3.8), F140L+A173V (10-17), H172Y+P252L (ND), A173V+T304I (5.8-20), T21I+L50F+A193P+S301P (29), T21I+S144A+T304I (11-28), T21I+C160F+A173V+V186A+T304I (28-29), T21I+A173V+T304I (15-16), and L50F+F140L+L167F+T304I (43-55).
Abbreviation: ND=no data.

Table 8 indicates Mpro substitutions and combinations of Mpro substitutions that have been found to reduce nirmatrelvir activity ≥3-fold (based on IC50 or Ki values) in biochemical assays using recombinant SARS-CoV-2 Mpro. Note that these Mpro substitutions were laboratory engineered and most were not observed in PAXLOVID-treated subjects in clinical trials. In addition, according to public sequence databases, most of these substitutions have not been observed in clinical isolates or have been observed but with global cumulative frequencies ≤0.002%. Thus, the clinical relevance of these substitutions is unclear. The following Mpro substitutions and combinations of Mpro substitutions emerged in cell culture in the presence of nirmatrelvir but conferred <3-fold reduced nirmatrelvir activity in biochemical assays: T21I, S46F, L50F, P108S, T135I, C160F, T169I, V186A, A191V, A193P, P252L, S301P, T304I, T21I+T304I, and L50F+T304I.

Table 8: SARS-CoV-2 Mpro Amino Acid Substitutions That Reduce Nirmatrelvir Activity ≥3-Fold in Biochemical Assays

Single Substitutions; (IC50/Ki value fold change in biochemical assay) | Y54A/C (3.0-25), F140A/L/S (1.2-230), G143S (3.6-148), S144A/F/G/M/W/Y (1.2-76), S144D/E/H/Q/T/V (81-480), S144K/L/P/R (1,165->5,319), H164N (1.9-6.7), M165D/F/G/T (5.7-51), M165H/K/P/R/W (>384), M165Y (3,838), E166A/G/K/L/Q (4.5-77), E166D/H/I/N/V/Y (143-708), E166R/V (>1,538-7,700), L167F (1.4-4.5), P168del (4.5-9.3), H172D/F/G/K/Q/Y (10-91), H172A/C/E/M/N/R/V/Y (114-858), H172I/L/S/T (1,172-6,740), A173S/V (4.1-52), R188G (38), Q189E/K (1.6-16), Q192A/C/D/E/F/G/H/I/K/L/P/R/S/T/V/W (5.0-61), Q192Y (>384), A260V (0.6-3.3), and V297A (3.0).
≥2 Substitutions; (IC50/Ki value fold change in biochemical assay) | T21I+S144A (20), T21I+E166V (120-11,000), T21I+A173V (15), L50F+E166V (100-4,500), T135I+T304I (5.1), F140L+A173V (95), S144A+T304I (28), E166V+L232R (5,700), P168del+A173V (170-536), H172Y+P252L (180), A173V+T304I (28), T21I+S144A+T304I (51), T21I+A173V+T304I (55), L50F+E166A+L167F (52-180), T21I+L50F+A193P+S301P (7.3), L50F+F140L+L167F+T304I (190), and T21I+C160F+A173V+V186A+T304I (28).

In Clinical Trials

Treatment-emergent substitutions were evaluated among subjects in clinical trials EPIC-HR/SR with sequence data available at both baseline and post-baseline visits (n=907 PAXLOVID-treated subjects, n=946 placebo-treated subjects). SARS-CoV-2 Mpro amino acid changes were classified as PAXLOVID treatment-emergent substitutions if they occurred at the same amino acid position in 3 or more PAXLOVID-treated subjects and were ≥2.5-fold more common in PAXLOVID-treated subjects than placebo-treated subjects. The following PAXLOVID treatment-emergent Mpro substitutions were observed: T98I/R/del(n=4), E166V (n=3), and W207L/R/del (n=4). In biochemical assays, the T98I and W207L/R substitutions did not affect nirmatrelvir activity (Ki value fold changes were 0.3 and 0.7/0.3, respectively), whereas the E166V substitution (which occurs at a Mpro-nirmatrelvir contact residue) reduced nirmatrelvir activity 187-7,700-fold. Within the Mpro cleavage sites, the following PAXLOVID treatment-emergent substitutions were observed: A5328S/V(n=7) and S6799A/P/Y (n=4). These cleavage site substitutions were not associated with the co-occurrence of any specific Mpro substitutions. In a cell culture replicon assay, the A5328S/V and S6799A substitutions did not affect nirmatrelvir activity (EC50 value fold changes were 0.3/0.2 and 0.7, respectively).

None of the treatment-emergent substitutions listed above in Mpro or Mpro cleavage sites occurred in PAXLOVID-treated subjects who experienced hospitalization. Thus, the clinical significance of these substitutions is unknown.

Viral RNA Rebound and Treatment-Emergent Substitutions

EPIC-HR and EPIC-SR were not designed to evaluate COVID-19 rebound; exploratory analyses were conducted to assess the relationship between PAXLOVID use and rebound in viral RNA shedding levels.

Post-treatment increases in SARS-CoV-2 RNA shedding levels in nasopharyngeal samples were observed on Day 10 and/or Day 14 in a subset of PAXLOVID and placebo recipients in EPIC-HR and EPIC-SR, irrespective of COVID-19 symptoms. The frequency of detection of post-treatment viral RNA rebound varied according to analysis parameters, but was generally similar among PAXLOVID and placebo recipients. A similar or smaller percentage of placebo recipients compared to PAXLOVID recipients had nasopharyngeal viral RNA results < lower limit of quantitation (LLOQ) at all study timepoints in both the treatment and post-treatment periods.

In EPIC-HR, of 59 PAXLOVID-treated subjects identified with post-treatment viral RNA rebound and with available viral sequence data, treatment-emergent substitutions in Mpro potentially reducing nirmatrelvir activity were detected in 2 (3%) subjects, including E166V in 1 subject and T304I in 1 subject. Both subjects had viral RNA shedding levels <LLOQ by Day 14.

Post-treatment viral RNA rebound was not associated with the primary clinical outcome of COVID-19 related hospitalization or death from any cause through Day 28 following the single 5-day course of PAXLOVID treatment. The clinical relevance of post-treatment increases in viral RNA following PAXLOVID or placebo treatment is unknown.

Cross-Resistance

Cross-resistance is not expected between nirmatrelvir and remdesivir or any other anti-SARS-CoV-2 agents with different mechanisms of action (i.e., agents that are not Mpro inhibitors).

13 NONCLINICAL TOXICOLOGY

13.1 Carcinogenesis, Mutagenesis, Impairment of Fertility

Nirmatrelvir

Carcinogenicity studies have not been conducted with nirmatrelvir.

Nirmatrelvir was negative for mutagenic or clastogenic activity in a battery of in vitro and in vivo assays including the Ames bacterial reverse mutation assay using S. typhimurium and E. coli, the in vitro micronucleus assay using human lymphoblastoid TK6 cells, and the in vivo rat micronucleus assays.

In a fertility and early embryonic development study, nirmatrelvir was administered orally to male and female rats at doses of 60, 200, or 1,000 mg/kg/day once daily beginning 14 days prior to mating, throughout the mating phase, and continued through GD 6 for females and for a total of 32 doses for males. There were no effects on fertility, reproductive performance, or early embryonic development at doses up to 1,000 mg/kg/day, resulting in systemic exposure (AUC24) approximately 5 times higher than exposure at the approved human dose of PAXLOVID.

Ritonavir

Carcinogenicity studies in mice and rats have been conducted on ritonavir. In male mice, at levels of 50, 100, or 200 mg/kg/day, there was a dose dependent increase in the incidence of both adenomas and combined adenomas and carcinomas in the liver. Based on AUC measurements, the exposure at the high dose was approximately 25 times higher than the exposure in humans at the approved human dose of PAXLOVID. No carcinogenic effects were observed in females at up to the highest dose tested, resulting in systemic exposure (AUC24) approximately 25 times higher than the exposure in humans at the approved human dose of PAXLOVID. In rats dosed at levels of 7, 15, or 30 mg/kg/day, there were no carcinogenic effects. In this study, the exposure at the high dose was approximately 5 times higher than the exposure in humans at the approved human dose of PAXLOVID.

Ritonavir was found to be negative for mutagenic or clastogenic activity in a battery of in vitro and in vivo assays including the Ames bacterial reverse mutation assay using S. typhimurium and E. coli, the mouse lymphoma assay, the mouse micronucleus test and chromosomal aberration assays in human lymphocytes.

Ritonavir produced no effects on fertility in rats at drug exposures approximately 18 (male) and 27 (female) times higher than the exposure in humans at the approved human dose of PAXLOVID.

14 CLINICAL STUDIES

14.1 Efficacy in Subjects at High Risk of Progression to Severe COVID-19 (EPIC-HR)

EPIC-HR (NCT04960202) was a Phase 2/3, randomized, double-blind, placebo-controlled trial in non-hospitalized symptomatic adult subjects with a laboratory confirmed diagnosis of SARS-CoV-2 infection. Eligible subjects were 18 years of age and older with at least 1 of the following risk factors for progression to severe disease: diabetes, overweight (BMI >25), chronic lung disease (including asthma), chronic kidney disease, current smoker, immunosuppressive disease or immunosuppressive treatment, cardiovascular disease, hypertension, sickle cell disease, neurodevelopmental disorders, active cancer, medically-related technological dependence, or were 60 years of age and older regardless of comorbidities. Subjects with COVID-19 symptom onset of ≤5 days were included in the study. Subjects were randomized (1:1) to receive PAXLOVID (nirmatrelvir/ritonavir 300 mg/100 mg) or placebo orally every 12 hours for 5 days. The trial excluded individuals with a history of prior COVID-19 infection or vaccination and excluded individuals taking any medications with clinically significant drug interactions with PAXLOVID. The primary efficacy endpoint was the proportion of subjects with COVID-19 related hospitalization or death from any cause through Day 28. The analysis was conducted in the modified intent-to-treat (mITT) analysis set [all treated subjects with onset of symptoms ≤3 days who at baseline did not receive nor were expected to receive COVID-19 therapeutic monoclonal antibody (mAb) treatment], the mITT1 analysis set (all treated subjects with onset of symptoms ≤5 days who at baseline did not receive nor were expected to receive COVID-19 therapeutic mAb treatment), and the mITT2 analysis set (all treated subjects with onset of symptoms ≤5 days).

A total of 2,113 subjects were randomized to receive either PAXLOVID or placebo. At baseline, mean age was 45 years; 51% were male; 71% were White, 15% were Asian, 9% were American Indian or Alaska Native, 4% were Black or African American, and 1% was missing or unknown; 41% were Hispanic or Latino; 67% of subjects had onset of symptoms ≤3 days before initiation of study treatment; 49% of subjects were serological negative at baseline; the mean (SD) baseline viral RNA in nasopharyngeal samples was 4.71 log10 copies/mL (2.89); 27% of subjects had a baseline viral RNA of ≥10^7 (log10 copies/mL); 6% of subjects either received or were expected to receive COVID-19 therapeutic monoclonal antibody treatment at the time of randomization and were excluded from the mITT and mITT1 analyses.

The baseline demographic and disease characteristics were balanced between the PAXLOVID and placebo groups.

The proportions of subjects who discontinued treatment due to an adverse event were 2.0% in the PAXLOVID group and 4.2% in the placebo group.

Table 9 provides results of the primary endpoint in mITT1 analysis population. For the primary endpoint, the relative risk reduction in the mITT1 analysis population for PAXLOVID compared to placebo was 86% (95% CI: 72%, 93%).

Table 9: COVID-19 Related Hospitalization or Death from Any Cause Through Day 28 in Non-Hospitalized Adults with COVID-19 (mITT1 Analysis Set): EPIC-HR
 | PAXLOVID (N=977) | Placebo (N=989)
COVID-19 Related Hospitalization or Death from Any Cause Through Day 28
n (%) | 9 (0.9%) | 64 (6.5%)
Reduction Relative to Placebo [The estimated cumulative proportion of subjects hospitalized or death by Day 28 was calculated for each treatment group using the Kaplan-Meier method, where subjects without hospitalization and death status through Day 28 were censored at the time of study discontinuation.] (95% CI), % | -5.6 (-7.3, -4.0)
COVID-19 Related Hospitalization Through Day 28, % | 9 (0.9%) | 63 (6.4%)
All-cause Mortality Through Day 28 [For the secondary endpoint of all-cause mortality through Week 24, there were 0 and 15 (1%) events in the PAXLOVID arm and placebo arm, respectively.] , % | 0 | 12 (1.2%)
Abbreviations: CI=confidence interval; COVID-19=coronavirus disease 2019; mAb=monoclonal antibody; mITT1=modified intent-to-treat 1 (all treated subjects with onset of symptoms ≤5 days who at baseline did not receive nor were expected to receive COVID-19 therapeutic mAb treatment).
The determination of primary efficacy was based on a planned interim analysis of 754 subjects in mITT population. The estimated risk reduction was -6.5% with a 95% CI of (-9.3%, -3.7%) and 2-sided p-value <0.0001.

Consistent results were observed in the mITT and mITT2 analysis populations.

Similar trends have been observed across subgroups of subjects (see Figure 1).

Figure 1: Subgroup Analysis of Adults with COVID-19 Dosed within 5 Days of Symptom Onset with COVID-19 Related Hospitalization or Death from Any Cause Through Day 28: EPIC-HR

Abbreviations: BMI=body mass index; COVID-19=coronavirus disease 2019; mAb=monoclonal antibody; mITT=modified intent-to-treat; SARS-CoV-2=severe acute respiratory syndrome coronavirus 2.
N=number of subjects in the category of the analysis set.
All categories are based on mITT1 population except for COVID-19 mAb treatment which is based on mITT2 population.
Seropositivity was defined if results were positive in either Elecsys anti-SARS-CoV-2 S or Elecsys anti-SARS-CoV-2 (N) assay.
The difference of the proportions in the 2 treatment groups and its 95% confidence interval based on normal approximation of the data are presented.

Among subjects who were SARS-CoV-2 seropositive at baseline, 1/490 (0.2%) PAXLOVID recipients versus 8/479 (1.7%) placebo recipients met the primary endpoint of COVID-19 related hospitalization or death from any cause through Day 28 [reduction relative to placebo -1.47% (-2.70%, -0.25%)].

14.2 Trial in Unvaccinated Subjects Without a Risk Factor for Progression to Severe COVID-19 or Subjects Fully Vaccinated Against COVID-19 With at Least One Factor for Progression to Severe COVID-19 (EPIC-SR)

PAXLOVID is not indicated for the treatment of COVID-19 in patients without a risk factor for progression to severe COVID-19.

EPIC-SR (NCT05011513) was a Phase 2/3, randomized, double-blind, placebo-controlled trial in non-hospitalized symptomatic adult subjects with a laboratory confirmed diagnosis of SARS-CoV-2 infection. Eligible subjects were 18 years of age or older with COVID-19 symptom onset of ≤5 days who were at standard risk for progression to severe disease. The trial included previously unvaccinated subjects with no risk factors for progression to severe disease or subjects fully vaccinated against COVID-19 (i.e., completed a primary vaccination series) with at least 1 of the risk factors for progression to severe disease as defined in EPIC-HR. Through the December 19, 2021, data cutoff, a total of 1,075 subjects were randomized (1:1) to receive PAXLOVID or placebo orally every 12 hours for 5 days; of these, 59% were fully vaccinated high-risk subjects.

The primary endpoint in this trial, the difference in time to sustained alleviation of all targeted COVID-19 signs and symptoms through Day 28 among PAXLOVID versus placebo recipients, was not met.

In an exploratory analysis of the subgroup of fully vaccinated subjects with at least 1 risk factor for progression to severe disease, a non-statistically significant numerical reduction relative to placebo for the secondary endpoint of COVID-19 related hospitalization or death from any cause through Day 28 was observed.

14.3 Post-Exposure Prophylaxis Trial

PAXLOVID is not indicated for the post-exposure prophylaxis of COVID-19.

In a double-blind, double-dummy, placebo-controlled trial, the efficacy of PAXLOVID when administered for 5 or 10 days as post-exposure prophylaxis of COVID-19 was evaluated. Eligible subjects were asymptomatic adults 18 years of age and older who were SARS-CoV-2 negative at baseline and who lived in the same household with symptomatic individuals with a recent diagnosis of SARS-CoV-2. A total of 2,736 subjects were randomized (1:1:1) to receive PAXLOVID orally every 12 hours for 5 days, PAXLOVID orally every 12 hours for 10 days, or placebo.

The primary endpoint for this trial was not met. The primary endpoint was the risk reduction between the 5-day and 10-day PAXLOVID regimens versus placebo in the proportion of subjects who developed RT-PCR or RAT-confirmed symptomatic SARS-CoV-2 infection through Day 14 who had a negative SARS-CoV-2 RT-PCR result at baseline. The proportion of subjects who had events through Day 14 was 2.6% for the 5-day PAXLOVID regimen, 2.4% for the 10-day PAXLOVID regimen, and 3.9% for placebo. There was not a statistically significant risk reduction versus placebo for either the 5-day or 10-day PAXLOVID regimen.

16 HOW SUPPLIED/STORAGE AND HANDLING

How Supplied

PAXLOVID is nirmatrelvir tablets co-packaged with ritonavir tablets. It is supplied in three different Dose Packs.

Nirmatrelvir tablets and ritonavir tablets are supplied in separate blister cavities within the same child-resistant blister card.

Dose Pack | Content | NDC | Description
300 mg nirmatrelvir; 100 mg ritonavir | Each Carton Contains: 30 tablets divided in 10 blister cards | 0069-5045-30 | Nirmatrelvir tablets: Oval, pink immediate-release, film-coated tablets debossed with "PFE" on one side and "3CL" on the other side. Ritonavir tablets: White to off-white, capsule-shaped, film-coated tablets debossed with "H" on one side and “R9” on the other side.
300 mg nirmatrelvir; 100 mg ritonavir | Each Carton Contains: 30 tablets divided in 10 blister cards | Or
300 mg nirmatrelvir; 100 mg ritonavir | Each Carton Contains: 30 tablets divided in 10 blister cards | 0069-5321-30 | Nirmatrelvir tablets: Oval, pink immediate-release, film-coated tablets debossed with "PFE" on one side and "3CL" on the other side. Ritonavir tablets: White film-coated ovaloid tablets debossed with "NK" on one side.
300 mg nirmatrelvir; 100 mg ritonavir | Each Blister Card Contains: 2 nirmatrelvir tablets (150 mg each) and 1 ritonavir tablet (100 mg) | 0069-5045-06 | Nirmatrelvir tablets: Oval, pink immediate-release, film-coated tablets debossed with "PFE" on one side and "3CL" on the other side. Ritonavir tablets: White to off-white, capsule-shaped, film-coated tablets debossed with "H" on one side and “R9” on the other side.
300 mg nirmatrelvir; 100 mg ritonavir | Each Blister Card Contains: 2 nirmatrelvir tablets (150 mg each) and 1 ritonavir tablet (100 mg) | Or
300 mg nirmatrelvir; 100 mg ritonavir | Each Blister Card Contains: 2 nirmatrelvir tablets (150 mg each) and 1 ritonavir tablet (100 mg) | 0069-5321-03 | Nirmatrelvir tablets: Oval, pink immediate-release, film-coated tablets debossed with "PFE" on one side and "3CL" on the other side. Ritonavir tablets: White film-coated ovaloid tablets debossed with "NK" on one side.
150 mg nirmatrelvir; 100 mg ritonavir | Each Carton Contains: 20 tablets divided in 10 blister cards | 0069-5317-20 | Nirmatrelvir tablets: Oval, pink immediate-release, film-coated tablets debossed with "PFE" on one side and "3CL" on the other side. Ritonavir tablets: White film-coated ovaloid tablets debossed with “NK” on one side.
150 mg nirmatrelvir; 100 mg ritonavir | Each Carton Contains: 20 tablets divided in 10 blister cards | Or
150 mg nirmatrelvir; 100 mg ritonavir |  | 0069-5434-20 | Nirmatrelvir tablets: Oval, pink immediate‑release, film‑coated tablets debossed with "PFE" on one side and "3CL" on the other side. Ritonavir tablets: White to off-white, capsule‑shaped, film‑coated tablets debossed with “H” on one side and “R9” on the other side.
150 mg nirmatrelvir; 100 mg ritonavir | Each Blister Card Contains:; 1 nirmatrelvir tablet (150 mg) and 1 ritonavir tablet (100 mg) | 0069-5317-02 | Nirmatrelvir tablets: Oval, pink immediate-release, film-coated tablets debossed with "PFE" on one side and "3CL" on the other side. Ritonavir tablets: White film-coated ovaloid tablets debossed with “NK” on one side.
150 mg nirmatrelvir; 100 mg ritonavir | Each Blister Card Contains:; 1 nirmatrelvir tablet (150 mg) and 1 ritonavir tablet (100 mg) | Or
150 mg nirmatrelvir; 100 mg ritonavir |  | 0069-5434-02 | Nirmatrelvir tablets: Oval, pink immediate‑release, film‑coated tablets debossed with "PFE" on one side and "3CL" on the other side. Ritonavir tablets: White to off-white, capsule‑shaped, film‑coated tablets debossed with “H” on one side and “R9” on the other side.
300 mg nirmatrelvir; 100 mg ritonavir (Day 1); 150 mg nirmatrelvir; 100 mg ritonavir (Days 2-5) | Each Carton Contains: 11 tablets in 1 blister card | 0069-0521-11 | Nirmatrelvir tablets: Oval, pink immediate-release, film-coated tablets debossed with "PFE" on one side and "3CL" on the other side. Ritonavir tablets: White film-coated ovaloid tablets debossed with “NK” on one side.
300 mg nirmatrelvir; 100 mg ritonavir (Day 1); 150 mg nirmatrelvir; 100 mg ritonavir (Days 2-5) | Each Carton Contains: 11 tablets in 1 blister card | Or
300 mg nirmatrelvir; 100 mg ritonavir (Day 1); 150 mg nirmatrelvir; 100 mg ritonavir (Days 2-5) | Each Carton Contains: 11 tablets in 1 blister card | 0069-5450-11 | Nirmatrelvir tablets: Oval, pink immediate‑release, film‑coated tablets debossed with "PFE" on one side and "3CL" on the other side. Ritonavir tablets: White to off-white, capsule‑shaped, film‑coated tablets debossed with “H” on one side and “R9” on the other side.
 | Each Blister Card Contains:; 6 nirmatrelvir tablets (150 mg) and 5 ritonavir tablets (100 mg) | 0069-0521-11 | Nirmatrelvir tablets: Oval, pink immediate-release, film-coated tablets debossed with "PFE" on one side and "3CL" on the other side. Ritonavir tablets: White film-coated ovaloid tablets debossed with “NK” on one side.
 | Each Blister Card Contains:; 6 nirmatrelvir tablets (150 mg) and 5 ritonavir tablets (100 mg) | Or
 | Each Blister Card Contains:; 6 nirmatrelvir tablets (150 mg) and 5 ritonavir tablets (100 mg) | 0069-5450-11 | Nirmatrelvir tablets: Oval, pink immediate‑release, film‑coated tablets debossed with "PFE" on one side and "3CL" on the other side. Ritonavir tablets: White to off-white, capsule‑shaped, film‑coated tablets debossed with “H” on one side and “R9” on the other side.

Storage and Handling

Store at USP controlled room temperature 20°C to 25°C (68°F to 77°F); excursions permitted between 15°C to 30°C (59°F to 86°F).

17 PATIENT COUNSELING INFORMATION

Advise the patient to read the FDA-approved patient labeling (Patient Information).

Drug Interactions

Inform patients that PAXLOVID may interact with certain drugs and is contraindicated for use with certain drugs; therefore, advise patients to report to their healthcare provider the use of any prescription, non-prescription medication, or herbal products [see Boxed Warning, Contraindications (4), Warnings and Precautions (5.1), and Drug Interactions (7)].

Hypersensitivity Reactions

Inform patients that anaphylaxis, serious skin reactions, and other hypersensitivity reactions have been reported, even following a single dose of PAXLOVID. Advise them to immediately discontinue the drug and to inform their healthcare provider at the first sign of a skin rash, hives or other skin reactions, difficulty in swallowing or breathing, any swelling suggesting angioedema (for example, swelling of the lips, tongue, face, tightness of the throat, hoarseness), or other symptoms of an allergic reaction [see Warnings and Precautions (5.2)].

Dosage Modification in Patients with Renal Impairment

Moderate Renal Impairment

To ensure appropriate dosing in patients with moderate renal impairment, instruct such patients that they will be taking one 150 mg nirmatrelvir tablet with one 100 mg ritonavir tablet together twice daily for 5 days [see Dosage and Administration (2.3)].

Severe Renal Impairment (Including Those Requiring Hemodialysis)

To ensure appropriate dosing in patients with severe renal impairment, including those requiring hemodialysis, instruct patients that they will be taking two 150 mg nirmatrelvir tablets with one 100 mg ritonavir tablet together once on Day 1, followed by one 150 mg nirmatrelvir tablet with one 100 mg ritonavir together once daily on Days 2-5. Instruct patients to take their dose at approximately the same time each day. On days when patients undergo hemodialysis, instruct them to take the PAXLOVID dose after hemodialysis [see Dosage and Administration (2.3)].

Administration Instructions

Inform patients to take PAXLOVID with or without food at approximately the same time each day as instructed. Advise patients to swallow all tablets for PAXLOVID whole and not to chew, break, or crush the tablets. Alert the patient of the importance of completing the full 5-day treatment course and to continuing isolation in accordance with public health recommendations to maximize viral clearance and minimize transmission of SARS-CoV-2. If the patient misses a dose of PAXLOVID within 8 hours of the time it is usually taken, the patient should take it as soon as possible and resume the normal dosing schedule. If the patient misses a dose by more than 8 hours, the patient should not take the missed dose and instead take the next dose at the regularly scheduled time. The patient should not double the dose to make up for a missed dose [see Dosage and Administration (2)].

This product’s labeling may have been updated. For the most recent prescribing information, please visit www.pfizer.com.

LAB-1523-7.0

PATIENT INFORMATION
PAXLOVID (pax-LO-vid)
(nirmatrelvir tablets; ritonavir tablets)
co-packaged for oral use

What is the most important information I should know about PAXLOVID?

PAXLOVID can interact with other medicines causing severe or life-threatening side effects or death. It is important to know the medicines that should not be taken with PAXLOVID.

Do not take PAXLOVID if:

- you are taking any of the following medicines:

- alfuzosin
- amiodarone
- apalutamide
- carbamazepine
- colchicine
- dihydroergotamine
- dronedarone
- eletriptan
- enzalutamide
- eplerenone
- ergotamine
- finerenone
- flecainide
- flibanserin

- ivabradine
- lomitapide
- lovastatin
- lumacaftor/ivacaftor
- lurasidone
- methylergonovine
- midazolam (oral)
- naloxegol
- phenobarbital
- phenytoin
- pimozide
- primidone
- propafenone

- quinidine
- ranolazine
- rifampin
- rifapentine
- St. John’s Wort (hypericum perforatum)
- sildenafil (Revatio®) for pulmonary arterial hypertension
- silodosin
- simvastatin
- suzetrigine
- tolvaptan
- triazolam
- ubrogepant
- voclosporin

These are not the only medicines that may cause serious or life-threatening side effects if taken with PAXLOVID. PAXLOVID may increase or decrease the levels of multiple other medicines. It is very important to tell your healthcare provider about all of the medicines you are taking because additional laboratory tests or changes in the dose of your other medicines may be necessary during treatment with PAXLOVID. Your healthcare provider may also tell you about specific symptoms to watch out for that may indicate that you need to stop or decrease the dose of some of your other medicines.

- you are allergic to nirmatrelvir, ritonavir, or any of the ingredients in PAXLOVID. See the end of this leaflet for a complete list of ingredients in PAXLOVID. See “What are the possible side effects of PAXLOVID?” for signs and symptoms of allergic reactions.

What is PAXLOVID?
PAXLOVID is a prescription medicine used to treat mild-to-moderate coronavirus disease 2019 (COVID-19) in adults who are at high risk for progression to severe COVID-19, including hospitalization or death.

PAXLOVID is not approved for use as pre-exposure or post-exposure treatment for prevention of COVID-19.

Before taking PAXLOVID, tell your healthcare provider about all of your medical conditions, including if you:

- have kidney problems. You may need a different dose or dosing schedule of PAXLOVID.
- have liver problems, including hepatitis.
- have Human Immunodeficiency Virus 1 (HIV-1) infection. PAXLOVID may lead to some HIV-1 medicines not working as well in the future.
- are pregnant or plan to become pregnant. It is not known if PAXLOVID can harm your unborn baby. Tell your healthcare provider right away if you are or if you become pregnant.
- are breastfeeding or plan to breastfeed. PAXLOVID can pass into your breast milk. Talk to your healthcare provider about the best way to feed your baby during treatment with PAXLOVID.

Tell your healthcare provider about all the medicines you take, including prescription and over-the-counter medicines, vitamins, and herbal supplements.

- Your healthcare provider can tell you if it is safe to take PAXLOVID with other medicines.
- You can ask your healthcare provider or pharmacist for a list of medicines that interact with PAXLOVID.
- Do not start taking a new medicine without telling your healthcare provider.

Tell your healthcare provider if you are taking combined birth control (hormonal contraceptive). PAXLOVID may affect how your hormonal contraceptives work. Females who are able to become pregnant should use another effective alternative form of contraception or an additional barrier method of contraception during treatment with PAXLOVID. Talk to your healthcare provider if you have any questions about contraceptive methods that might be right for you.

How should I take PAXLOVID?

- Take PAXLOVID exactly as your healthcare provider tells you to take it.
- PAXLOVID consists of 2 medicines: nirmatrelvir tablets and ritonavir tablets. The 2 medicines are taken together for 5 days.
  - Nirmatrelvir is an oval, pink tablet.
  - Ritonavir is a white or off-white tablet.
- PAXLOVID is available in 3 Dose Packs (see Figures A, B, and C below). Your healthcare provider will prescribe the PAXLOVID Dose Pack that is right for you. Follow the instruction for the Dose Pack you receive.
- If you have kidney disease, your healthcare provider may prescribe a lower dose (see Figures B and C). Talk to your healthcare provider to make sure you receive the correct Dose Pack.

Figure A

If you are prescribed PAXLOVID 300 mg; 100 mg Dose Pack
Each dose contains 3 tablets taken together twice daily

How to take PAXLOVID 300 mg; 100 mg Dose Pack

Morning Dose:
Take the 2 pink nirmatrelvir tablets and
1 white to off-white ritonavir tablet together.

Bedtime Dose:
Take the 2 pink nirmatrelvir tablets and
1 white to off-white ritonavir tablet together.

Figure B

If you are prescribed PAXLOVID 150 mg; 100 mg Dose Pack
Each dose contains 2 tablets taken together twice daily

How to take PAXLOVID 150 mg; 100 mg Dose Pack

Morning Dose:
Take the 1 pink nirmatrelvir tablet and
1 white ritonavir tablet together.

Bedtime Dose:
Take the 1 pink nirmatrelvir tablet and
1 white ritonavir tablet together.

Figure C

If you are prescribed PAXLOVID 300 mg; 100 mg (Day 1) and 150 mg; 100 mg (Days 2-5)
Each dose is taken together once daily; on days of dialysis take PAXLOVID after receiving dialysis

How to take PAXLOVID 300 mg; 100 mg (Day 1) and 150 mg; 100 mg (Days 2-5)

Day 1 (First Day):

Take the 2 pink nirmatrelvir tablets and
1 white ritonavir tablet together
(Blue part of the blister card).

Days 2-5:

Take the 1 pink nirmatrelvir tablet and

1 white ritonavir tablet together

(Pink part of the blister card).

- Do not remove your PAXLOVID tablets from the blister card before you are ready to take your dose.
- If you are taking PAXLOVID tablets twice daily (Figure A or Figure B), take your first dose of PAXLOVID in the morning or at bedtime, depending on when you pick up your prescription, or as your healthcare provider tells you to. Take your doses at around the same time each day.
- If you have severe kidney disease and are taking PAXLOVID tablets once daily (Figure C), follow the daily dose instruction on the blister card. Take your dose at around the same time each day.
- Swallow the tablets whole. Do not chew, break, or crush the tablets.
- Take PAXLOVID with or without food.
- Do not stop taking PAXLOVID without talking to your healthcare provider, even if you feel better.
- If you miss a dose of PAXLOVID within 8 hours of the time it is usually taken, take it as soon as you remember. If you miss a dose by more than 8 hours, skip the missed dose and take the next dose at your regular time. Do not take 2 doses of PAXLOVID at the same time.
- If you take too much PAXLOVID, call your healthcare provider or go to the nearest hospital emergency room right away.
- If you are taking a ritonavir- or cobicistat-containing medicine to treat hepatitis C or HIV-1 infection, you should continue to take your medicine as prescribed by your healthcare provider.

Talk to your healthcare provider if you do not feel better or if you feel worse after 5 days.

What are the possible side effects of PAXLOVID?

PAXLOVID may cause serious side effects, including:

- Allergic reactions, including severe allergic reactions (anaphylaxis) have happened during treatment with PAXLOVID. Stop taking PAXLOVID and get medical help right away if you get any of the following symptoms of an allergic reaction:

- skin rash, hives, blisters or peeling skin
- painful sores or ulcers in the mouth, nose, throat or genital area
- swelling of the mouth, lips, tongue or face

- trouble swallowing or breathing
- throat tightness
- hoarseness

- Liver problems. Tell your healthcare provider right away if you get any of the following signs and symptoms of liver problems during treatment with PAXLOVID:

- loss of appetite
- yellowing of your skin and the white of eyes
- dark-colored urine

- pale colored stools
- itchy skin
- stomach-area (abdominal) pain

The most common side effects of PAXLOVID include: altered sense of taste (such as metallic, bitter taste) and diarrhea.

Other possible side effects include:

- headache
- vomiting
- abdominal pain
- nausea
- high blood pressure
- feeling generally unwell

These are not all of the possible side effects of PAXLOVID. For more information, ask your healthcare provider or pharmacist.

Call your doctor for medical advice about side effects. You may report side effects to FDA at 1-800-FDA-1088.

How should I store PAXLOVID?

- Store PAXLOVID at room temperature between 68°F to 77°F (20°C to 25°C).

Keep PAXLOVID and all medicines out of the reach of children.

General information about the safe and effective use of PAXLOVID.
Medicines are sometimes prescribed for purposes other than those listed in a Patient Information leaflet. Do not use PAXLOVID for a condition for which it was not prescribed. Do not give PAXLOVID to other people, even if they have the same symptoms that you have. It may harm them. You can ask your healthcare provider or pharmacist for more information about PAXLOVID that is written for health professionals.

What are the ingredients in PAXLOVID?
Active ingredient: nirmatrelvir and ritonavir
Nirmatrelvir inactive ingredients: colloidal silicon dioxide, croscarmellose sodium, lactose monohydrate, microcrystalline cellulose, and sodium stearyl fumarate. Film-coating contains: hydroxy propyl methylcellulose, iron oxide red, polyethylene glycol, and titanium dioxide.
Ritonavir inactive ingredients: anhydrous dibasic calcium phosphate, colloidal silicon dioxide, copovidone, sodium stearyl fumarate, and sorbitan monolaurate. The film coating may contain: colloidal anhydrous silica, colloidal silicon dioxide, hydroxypropyl cellulose, hypromellose, polyethylene glycol, polysorbate 80, talc, and titanium dioxide.

LAB-1524-5.0
For more information, go to www.pfizer.com or call 1-800-438-1985.

This Patient Information has been approved by the U.S. Food and Drug Administration. Revised: 02/2026

PRINCIPAL DISPLAY PANEL - 3 Tablet Blister Pack - 0069-5045

NDC 0069-5045-06

PAXLOVID™
(nirmatrelvir tablets;
ritonavir tablets),
co-packaged for oral use
300 mg; 100 mg

nirmatrelvir
tablet
(150 mg)

Take these
3 tablets
together

ritonavir
tablet
(100 mg)

nirmatrelvir
tablet
(150 mg)

Rx only

PAA232044
Dist. by Pfizer Labs
Div. of Pfizer Inc., NY, NY 10001

LOT:
EXP:

PRINCIPAL DISPLAY PANEL - Kit Carton - 0069-5045

Pfizer
NDC 0069-5045-30

PAXLOVID™
(nirmatrelvir tablets; ritonavir tablets),
co-packaged for oral use

300 mg; 100 mg Dose Pack

Take all 3 tablets from one blister
card together, twice daily (in morning
and at bedtime) for 5 days.

Each carton contains 30 tablets in 10 blister cards
Each blister card contains 3 tablets:

- 2 nirmatrelvir tablets (150 mg each)
- 1 ritonavir tablet (100 mg each)

Note to pharmacist:
Do not cover ALERT box with pharmacy label.

ALERT: Find out about medicines that
should NOT be taken with Paxlovid

Rx only

PRINCIPAL DISPLAY PANEL - 3 Tablet Blister Pack - 0069-5321

NDC 0069-5321-03

PAXLOVID™
(nirmatrelvir tablets;
ritonavir tablets),
co-packaged for oral use
300 mg; 100 mg

nirmatrelvir
tablet
(150 mg)

Take these
3 tablets
together

ritonavir
tablet
(100 mg)

nirmatrelvir
tablet
(150 mg)

Rx only

PAA206981
Dist. by Pfizer Labs
Div. of Pfizer Inc., NY, NY 10001

LOT:
EXP:

PRINCIPAL DISPLAY PANEL - Kit Carton - 0069-5321

Pfizer
NDC 0069-5321-30

PAXLOVID™
(nirmatrelvir tablets; ritonavir tablets),
co-packaged for oral use

300 mg; 100 mg Dose Pack

Take all 3 tablets from one blister
card together, twice daily (in morning
and at bedtime) for 5 days.

Each carton contains 30 tablets in 10 blister cards
Each blister card contains 3 tablets:

- 2 nirmatrelvir tablets (150 mg each)
- 1 ritonavir tablet (100 mg each)

Note to pharmacist:
Do not cover ALERT box with pharmacy label.

ALERT: Find out about medicines that
should NOT be taken with Paxlovid

Rx only

PRINCIPAL DISPLAY PANEL - 2 Tablet Blister Pack - 0069-5317

NDC 0069-5317-02
Rx only

nirmatrelvir
tablet
(150 mg)

This cavity
intentionally
left empty

Take these
2 tablets
together

PAXLOVID™
(nirmatrelvir tablets;
ritonavir tablets),
co-packaged for oral use
150 mg; 100 mg

This cavity
intentionally
left empty

ritonavir
tablet
(100 mg)

Dist. by Pfizer Labs
Div. of Pfizer Inc., NY, NY 10001

LOT:
EXP:
PAA206982

PRINCIPAL DISPLAY PANEL - Kit Carton - 0069-5317

Pfizer
NDC 0069-5317-20

PAXLOVID™
(nirmatrelvir tablets; ritonavir tablets),
co-packaged for oral use

150 mg; 100 mg Dose Pack

Take both tablets from one blister
card together, twice daily (in morning
and at bedtime) for 5 days.

Each carton contains 20 tablets in 10 blister cards
Each blister card contains 2 tablets:

- 1 nirmatrelvir tablet (150 mg each)
- 1 ritonavir tablet (100 mg each)

Note to pharmacist:
Do not cover ALERT box with pharmacy label.

ALERT: Find out about medicines that
should NOT be taken with Paxlovid

Rx only

PRINCIPAL DISPLAY PANEL - 11 Tablet Blister Pack - 0069-0521

Day 1 (300 mg; 100 mg)
Your first day’s dose. Take these 3 tablets together

nirmatrelvir
tablet
(150 mg)
nirmatrelvir
tablet
(150 mg)
ritonavir
tablet
(100 mg)

NDC 0069-0521-11
Rx only
PAXLOVID™
(nirmatrelvir tablets; ritonavir tablets), co-packaged for oral use

nirmatrelvir
tablet
(150 mg)
Day 2 (150 mg; 100 mg)
Take these
2 tablets together
ritonavir
tablet
(100 mg)

PAA228321

nirmatrelvir
tablet
(150 mg)
Day 3 (150 mg; 100 mg)
Take these
2 tablets together
ritonavir
tablet
(100 mg)

nirmatrelvir
tablet
(150 mg)
Day 4 (150 mg; 100 mg)
Take these
2 tablets together
ritonavir
tablet
(100 mg)

nirmatrelvir
tablet
(150 mg)
Day 5 (150 mg; 100 mg)
Take these
2 tablets together
ritonavir
tablet
(100 mg)

Dist. by Pfizer Labs, Div. of Pfizer Inc., NY, NY 10001

PRINCIPAL DISPLAY PANEL – Kit Carton - 0069-0521

Pfizer
NDC 0069-0521-11

PAXLOVID™
(nirmatrelvir tablets; ritonavir tablets),
co-packaged for oral use

300 mg; 100 mg (Day 1)
150 mg; 100 mg (Days 2 – 5)

Day 1:
Take 2 nirmatrelvir tablets and
1 ritonavir tablet together
Days 2 - 5:
Take 1 nirmatrelvir tablet and
1 ritonavir tablet together

Carton contains 1 blister card with 11 tablets:

- 6 nirmatrelvir tablets (150 mg each)
- 5 ritonavir tablets (100 mg each)

Note to pharmacist:
Do not cover ALERT box with pharmacy label.

ALERT: Find out about medicines that
should NOT be taken with Paxlovid

Rx only

PRINCIPAL DISPLAY PANEL - 2 Tablet Blister Pack - 0069-5434

NDC 0069-5434-02
Rx only

nirmatrelvir
tablet
(150 mg)

This cavity
intentionally
left empty

Take these
2 tablets
together

PAXLOVID™
(nirmatrelvir tablets;
ritonavir tablets),
co-packaged for oral use
150 mg; 100 mg

This cavity
intentionally
left empty

ritonavir
tablet
(100 mg)

Dist. by Pfizer Labs
Div. of Pfizer Inc., NY, NY 10001

LOT:
EXP:
PAA232045

PRINCIPAL DISPLAY PANEL - Kit Carton - 0069-5434

Pfizer
NDC 0069-5434-20

PAXLOVID™
(nirmatrelvir tablets; ritonavir tablets),
co-packaged for oral use

150 mg; 100 mg Dose Pack

Take both tablets from one blister
card together, twice daily (in morning
and at bedtime) for 5 days.

Each carton contains 20 tablets in 10 blister cards
Each blister card contains 2 tablets:

- 1 nirmatrelvir tablet (150 mg each)
- 1 ritonavir tablet (100 mg each)

Note to pharmacist:
Do not cover ALERT box with pharmacy label.

ALERT: Find out about medicines that
should NOT be taken with Paxlovid

Rx only

PRINCIPAL DISPLAY PANEL - 11 Tablet Blister Pack - 0069-5450

Day 1 (300 mg; 100 mg)
Your first day’s dose. Take these 3 tablets together

nirmatrelvir
tablet
(150 mg)
nirmatrelvir
tablet
(150 mg)
ritonavir
tablet
(100 mg)

NDC 0069-5450-11
Rx only
PAXLOVID™
(nirmatrelvir tablets; ritonavir tablets), co-packaged for oral use

nirmatrelvir
tablet
(150 mg)
Day 2 (150 mg; 100 mg)
Take these
2 tablets together
ritonavir
tablet
(100 mg)

PAA228417

nirmatrelvir
tablet
(150 mg)
Day 3 (150 mg; 100 mg)
Take these
2 tablets together
ritonavir
tablet
(100 mg)

nirmatrelvir
tablet
(150 mg)
Day 4 (150 mg; 100 mg)
Take these
2 tablets together
ritonavir
tablet
(100 mg)

nirmatrelvir
tablet
(150 mg)
Day 5 (150 mg; 100 mg)
Take these
2 tablets together
ritonavir
tablet
(100 mg)

Dist. by Pfizer Labs, Div. of Pfizer Inc., NY, NY 10001

PRINCIPAL DISPLAY PANEL – Kit Carton - 0069-5450

Pfizer
NDC 0069-5450-11

PAXLOVID™
(nirmatrelvir tablets; ritonavir tablets),
co-packaged for oral use

300 mg; 100 mg (Day 1)
150 mg; 100 mg (Days 2 – 5)

Day 1:
Take 2 nirmatrelvir tablets and
1 ritonavir tablet together
Days 2 - 5:
Take 1 nirmatrelvir tablet and
1 ritonavir tablet together

Carton contains 1 blister card with 11 tablets:

- 6 nirmatrelvir tablets (150 mg each)
- 5 ritonavir tablets (100 mg each)

Note to pharmacist:
Do not cover ALERT box with pharmacy label.

ALERT: Find out about medicines that
should NOT be taken with Paxlovid

Rx only